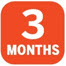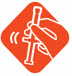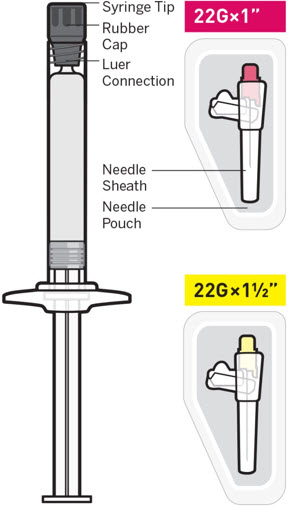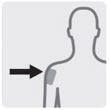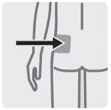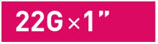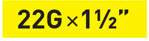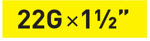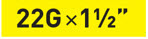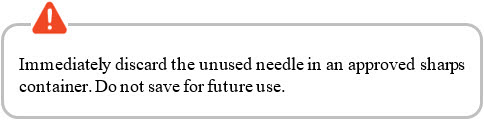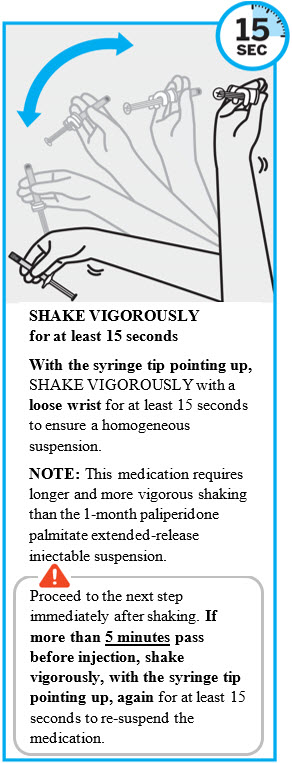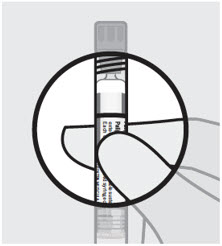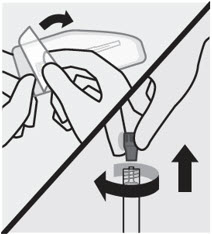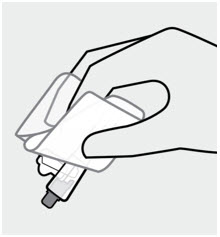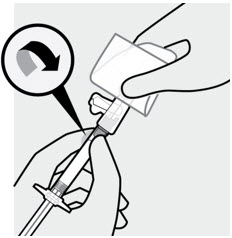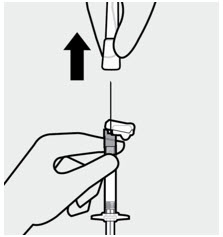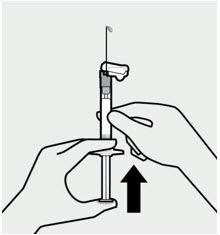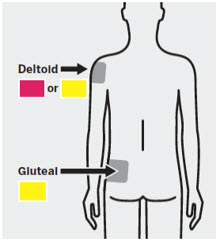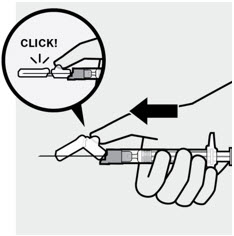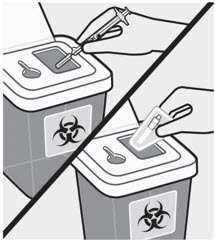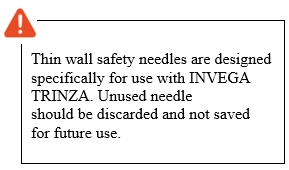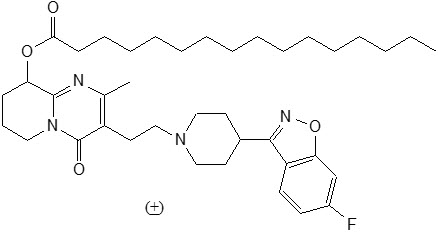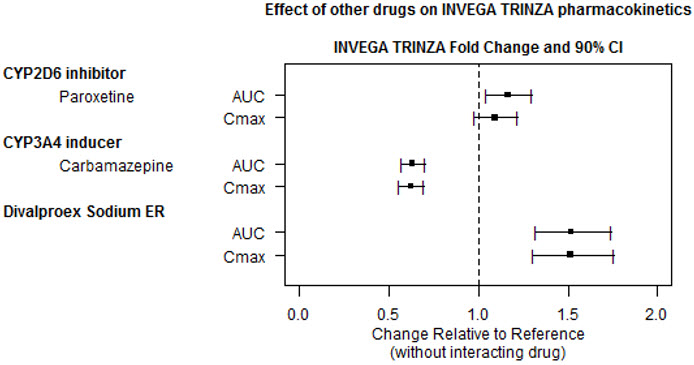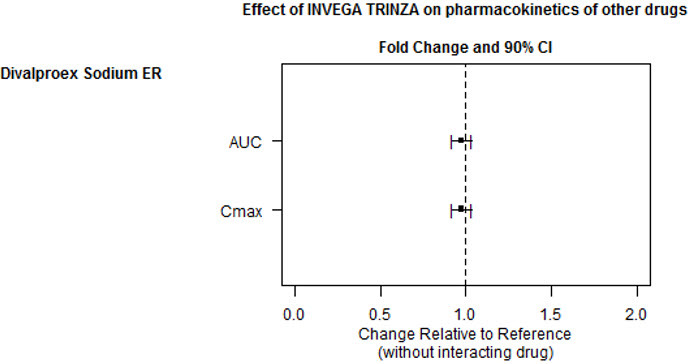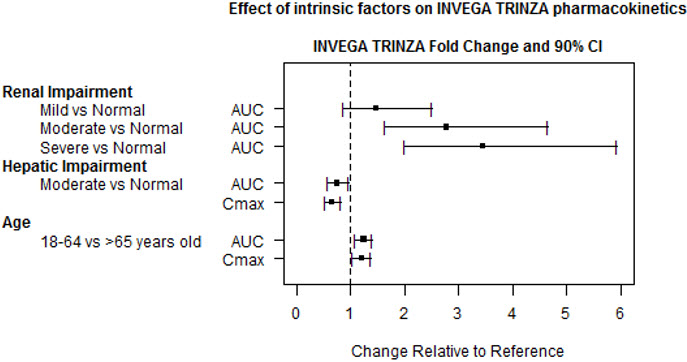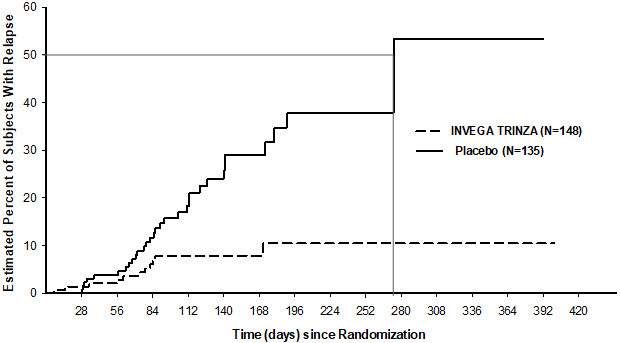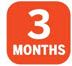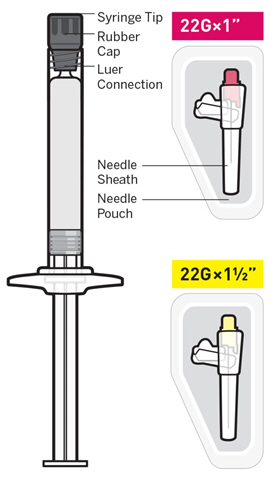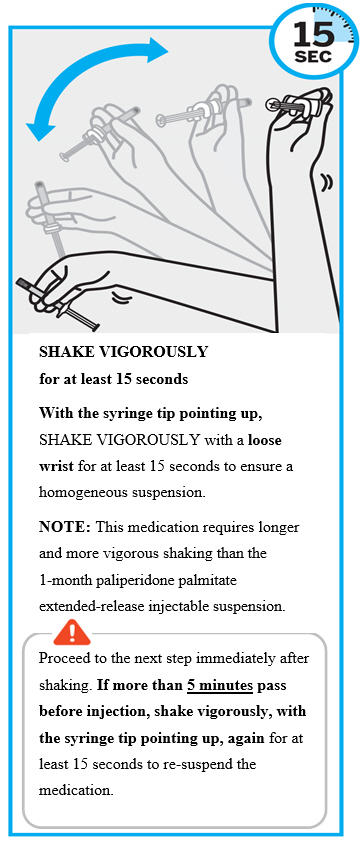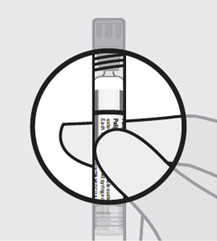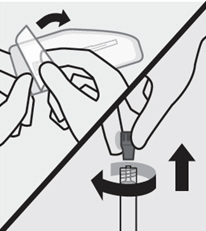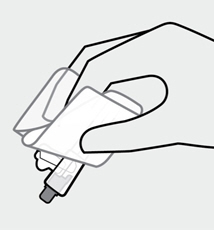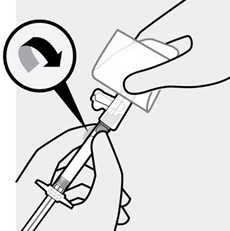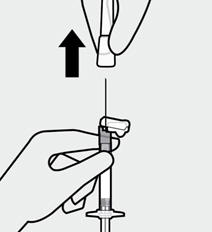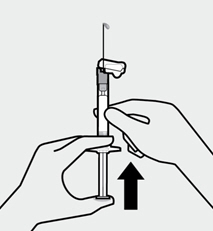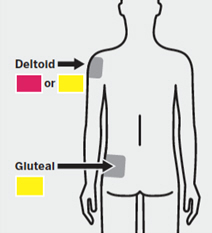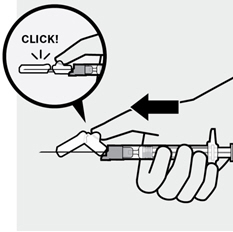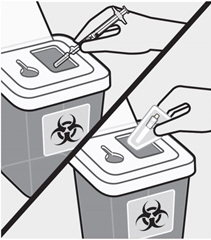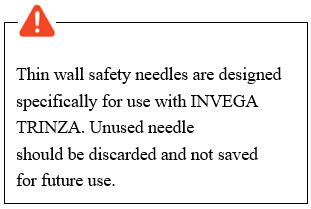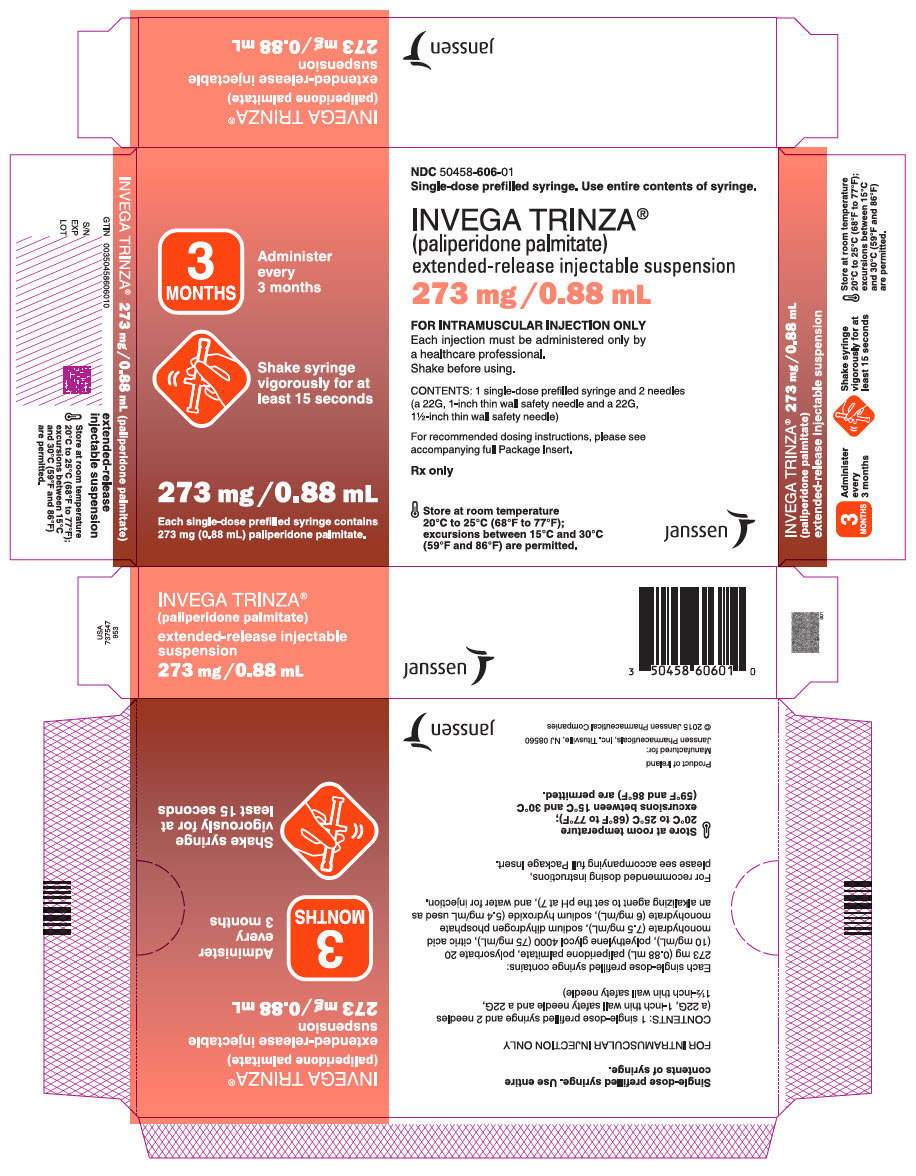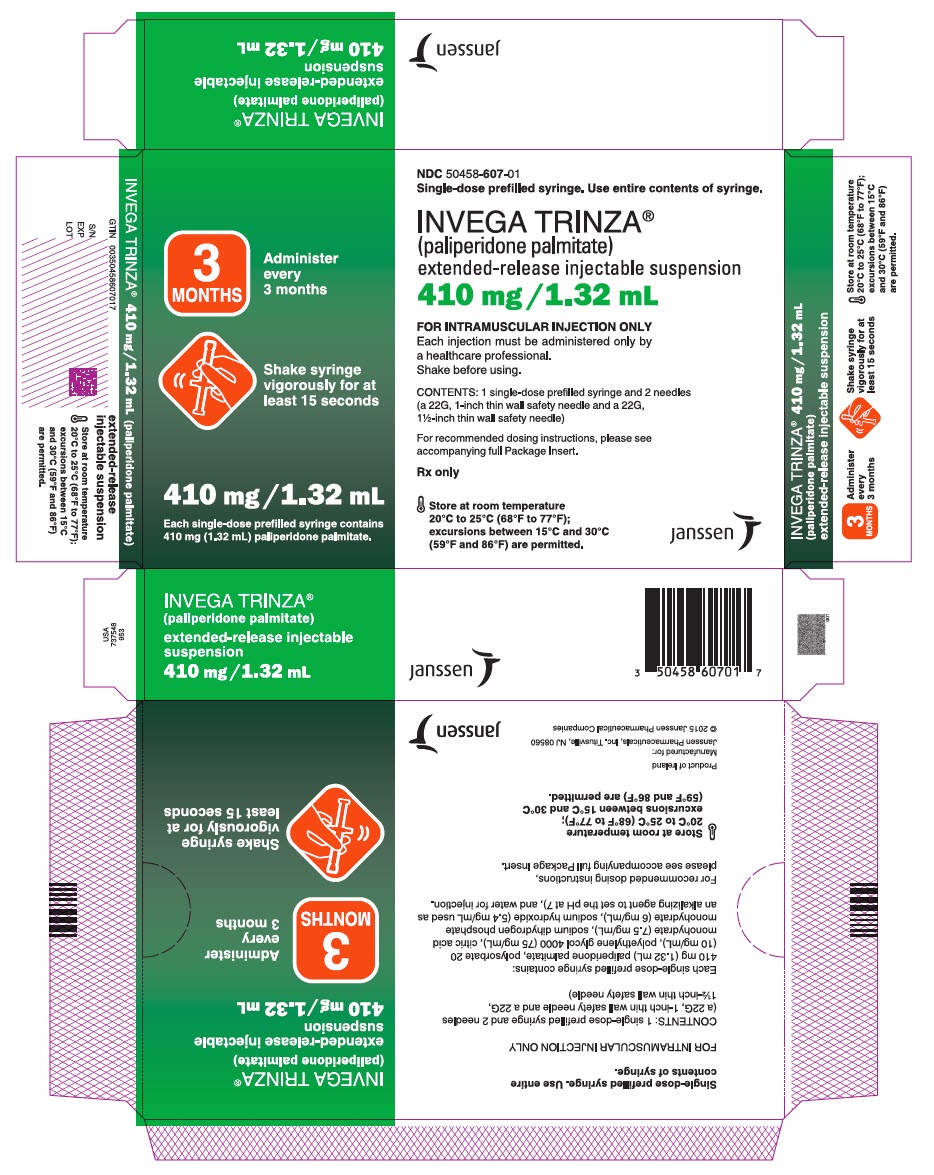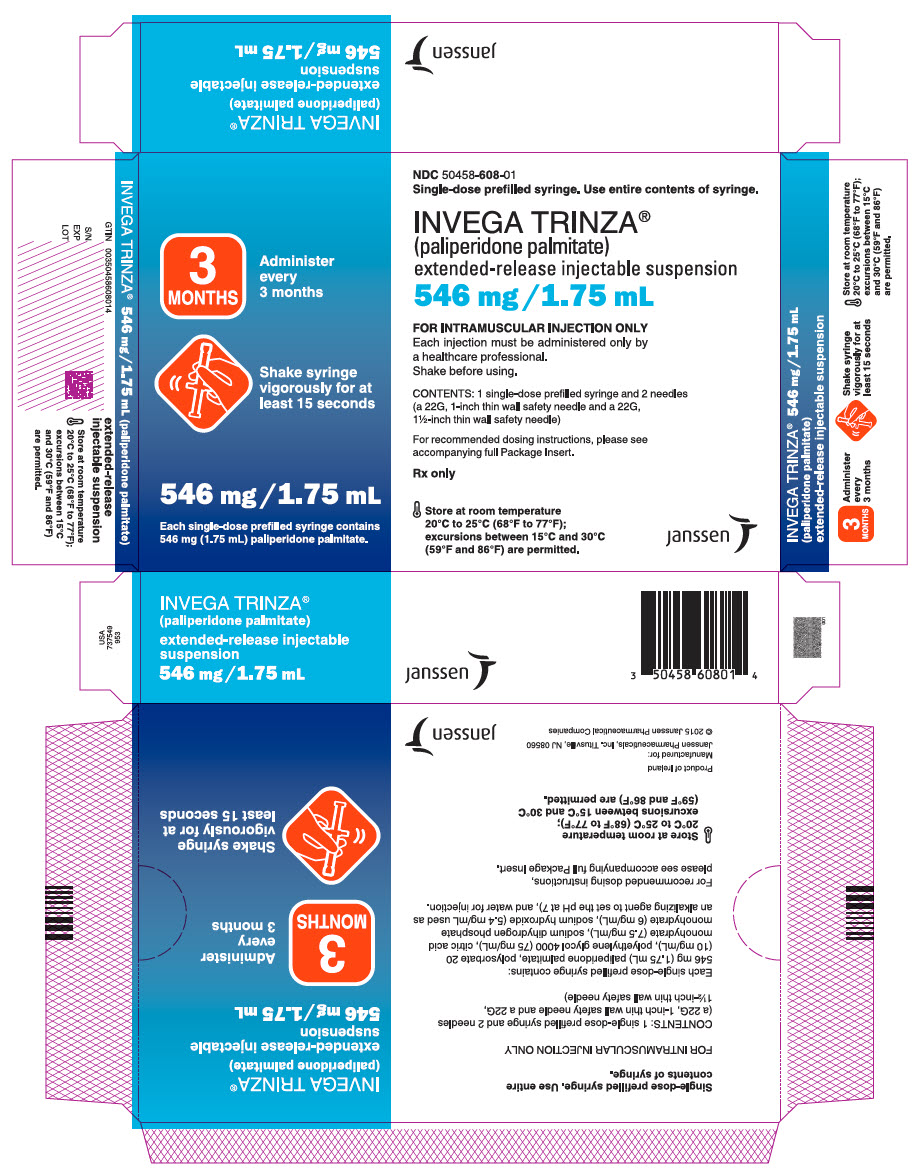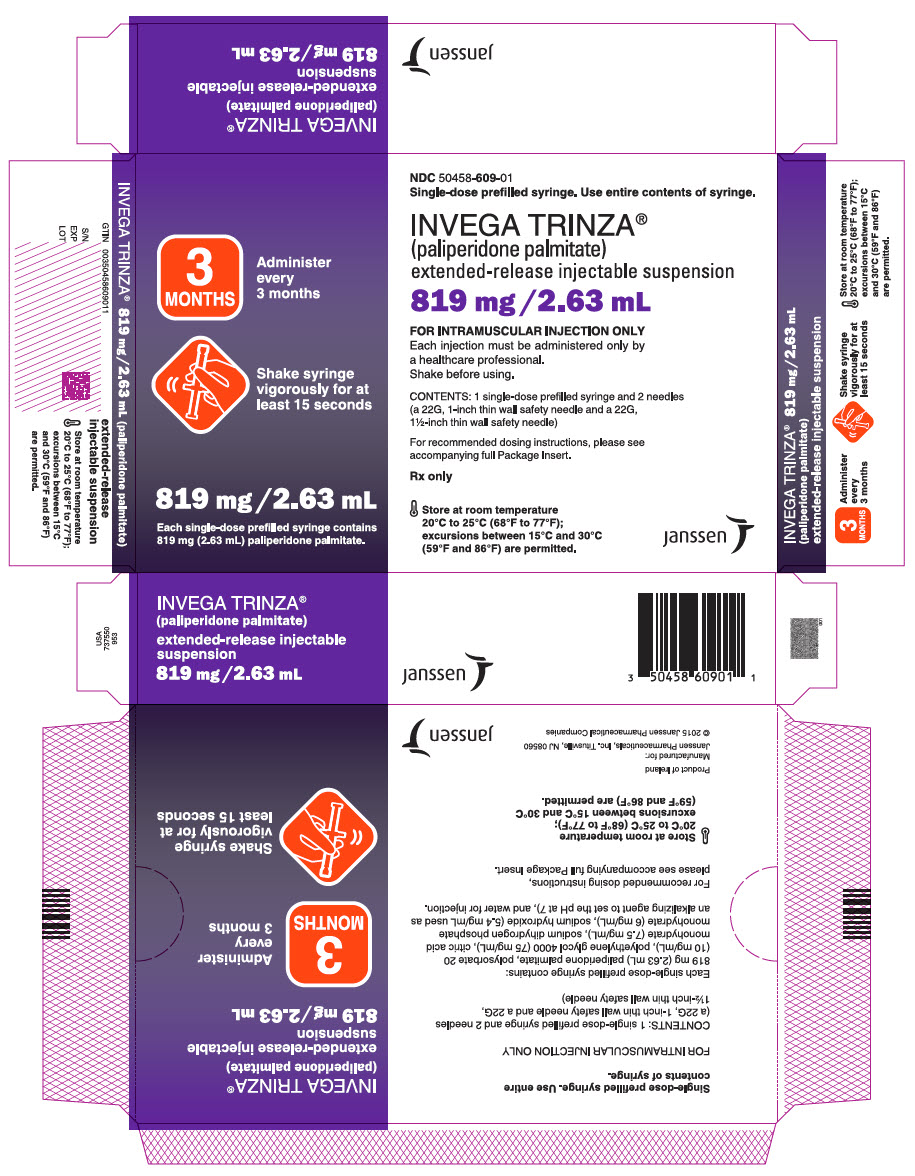 DRUG LABEL: INVEGA TRINZA
NDC: 50458-606 | Form: INJECTION, SUSPENSION, EXTENDED RELEASE
Manufacturer: Janssen Pharmaceuticals, Inc
Category: prescription | Type: HUMAN PRESCRIPTION DRUG LABEL
Date: 20250214

ACTIVE INGREDIENTS: PALIPERIDONE PALMITATE 273 mg/0.88 mL
INACTIVE INGREDIENTS: POLYSORBATE 20; POLYETHYLENE GLYCOL 4000; CITRIC ACID MONOHYDRATE; SODIUM HYDROXIDE; WATER

HIGHLIGHTS OF PRESCRIBING INFORMATION

These highlights do not include all the information needed to use INVEGA TRINZA safely and effectively. See full prescribing information for INVEGA TRINZA.
INVEGA TRINZA®(paliperidone palmitate) extended-release injectable suspension, for intramuscular use
Initial U.S. Approval: 2006

WARNING: INCREASED MORTALITY IN ELDERLY PATIENTS WITH DEMENTIA-RELATED PSYCHOSIS

See full prescribing information for complete boxed warning.

Elderly patients with dementia-related psychosis treated with antipsychotic drugs are at an increased risk of death. INVEGA TRINZA is not approved for use in patients with dementia-related psychosis. (5.1)

RECENT MAJOR CHANGES

Dosage and Administration (2.5, 2.8) | 9/2024
Warnings and Precautions (5.10) | 1/2025

1 INDICATIONS AND USAGE

INVEGA TRINZA, a 3-month injection, is an atypical antipsychotic indicated for the treatment of schizophrenia in patients after they have been adequately treated with INVEGA SUSTENNA (1-month paliperidone palmitate extended-release injectable suspension) for at least four months. (1)

2 DOSAGE AND ADMINISTRATION

- Use INVEGA TRINZA only after the patient has been adequately treated with the 1-month paliperidone palmitate extended-release injectable suspension for at least four months. (2.2)
- INVEGA TRINZA should be administered once every 3 months. (2.1)
- For intramuscular injection only. (2.1)
- Each injection must be administered only by a healthcare professional. (2.1)
- For deltoid injection: For patients weighing less than 90 kg, use the 1-inch 22 gauge thin wall needle. For patients weighing 90 kg or more, use the 1½-inch 22 gauge thin wall needle.
- For gluteal injection: Regardless of patient weight, use the1½-inch 22 gauge thin wall needle.
- Prior to administration, shake the prefilled syringe vigorously for at least 15 seconds within 5 minutes prior to administration to ensure a homogeneous suspension. (2.1)
- Initiate INVEGA TRINZA when the next 1-month paliperidone palmitate dose is scheduled with an INVEGA TRINZA dose based on the previous 1-month injection dose as shown below. (2.2)
  INVEGA TRINZA Doses for Adult Patients Adequately Treated with INVEGA SUSTENNA
  If the Last Dose of INVEGA SUSTENNA is: | Initiate INVEGA TRINZA at the Following Dose:
  78 mg | 273 mg
  117 mg | 410 mg
  156 mg | 546 mg
  234 mg | 819 mg
  Conversion from the INVEGA SUSTENNA 39 mg dose was not studied.
- Missed Doses: Missing doses of INVEGA TRINZA should be avoided. To manage missed doses on exceptional occasions, refer to the Full Prescribing Information. (2.3)
- Moderate to severe renal impairment (creatinine clearance < 50 mL/min): INVEGA TRINZA is not recommended. (2.5)
- Mild renal impairment (creatinine clearance ≥ 50 mL/min to < 80 mL/min): Adjust dosage and stabilize the patient using INVEGA SUSTENNA, then transition to INVEGA TRINZA. See above table. (2.5)

3 DOSAGE FORMS AND STRENGTHS

Extended-release injectable suspension: 273 mg/0.88 mL, 410 mg/1.32 mL, 546 mg/1.75 mL, or 819 mg/2.63 mL (3)

4 CONTRAINDICATIONS

Known hypersensitivity to paliperidone, risperidone, or to any excipients in INVEGA TRINZA. (4)

5 WARNINGS AND PRECAUTIONS

- Cerebrovascular Adverse Reactions, Including Stroke, in Elderly Patients with Dementia-Related Psychosis: Increased incidence of cerebrovascular adverse reactions (e.g. stroke, transient ischemic attack, including fatalities). INVEGA TRINZA is not approved for use in patients with dementia-related psychosis (5.2)
- Neuroleptic Malignant Syndrome: Manage with immediate discontinuation of drug and close monitoring (5.3)
- QT Prolongation: Avoid use with drugs that also increase QT interval and in patients with risk factors for prolonged QT interval (5.4)
- Tardive Dyskinesia: Discontinue drug if clinically appropriate (5.5)
- Metabolic Changes: Atypical antipsychotic drugs have been associated with metabolic changes that may increase cardiovascular/cerebrovascular risk. These metabolic changes include:
  - Hyperglycemia and Diabetes Mellitus: Monitor for symptoms of hyperglycemia including polydipsia, polyuria, polyphagia, and weakness. Monitor glucose regularly in patients with diabetes or at risk for diabetes. (5.6)
  - Dyslipidemia: Undesirable alterations have been observed. (5.6)
  - Weight Gain: Significant weight gain has been reported. Monitor weight gain. (5.6)
- Orthostatic Hypotension and Syncope: Use with caution in patients with known cardiovascular or cerebrovascular disease and patients predisposed to hypotension (5.7)
- Leukopenia, Neutropenia, and Agranulocytosis:Monitor complete blood count in patients with a history of a clinically significant low white blood cell count (WBC) or a drug-induced leukopenia/neutropenia. Consider discontinuation if clinically significant decline in WBC in the absence of other causative factors (5.9)
- Hyperprolactinemia: Prolactin elevations occur and persist during chronic administration (5.10)
- Potential for Cognitive and Motor Impairment: Use caution when operating machinery (5.11)
- Seizures: Use cautiously in patients with a history of seizures or with conditions that lower the seizure threshold (5.12)

6 ADVERSE REACTIONS

The most common adverse reactions (incidence ≥ 5% and occurring at least twice as often as placebo) were injection site reaction, weight increased, headache, upper respiratory tract infection, akathisia, and parkinsonism. (6)

To report SUSPECTED ADVERSE REACTIONS, contact Janssen Pharmaceuticals, Inc. at 1-800-526-7736 or FDA at 1-800-FDA-1088 or www.fda.gov/medwatch

7 DRUG INTERACTIONS

Strong CYP3A4/P-glycoprotein (P-gp) inducers: Avoid using a strong inducer of CYP3A4 and/or P-gp (e.g., carbamazepine, rifampin, St John's Wort) during a dosing interval for INVEGA TRINZA. If administering a strong inducer is necessary, consider managing the patient using paliperidone extended release tablets. (7.2, 12.3)

8 USE IN SPECIFIC POPULATIONS

Pregnancy: May cause extrapyramidal and/or withdrawal symptoms in neonates with third trimester exposure. (8.1)

FULL PRESCRIBING INFORMATION

WARNING: INCREASED MORTALITY IN ELDERLY PATIENTS WITH DEMENTIA-RELATED PSYCHOSIS

Elderly patients with dementia-related psychosis treated with antipsychotic drugs are at an increased risk of death. INVEGA TRINZA is not approved for use in patients with dementia-related psychosis. [see Warnings and Precautions (5.1)] .

1 INDICATIONS AND USAGE

INVEGA TRINZA (paliperidone palmitate), a 3-month injection, is indicated for the treatment of schizophrenia in patients after they have been adequately treated with INVEGA SUSTENNA (1-month paliperidone palmitate extended-release injectable suspension) for at least four months [see Dosage and Administration (2.2)and Clinical Studies (14)] .

2 DOSAGE AND ADMINISTRATION

2.1 Administration Instructions

INVEGA TRINZA should be administered once every 3 months.

Each injection must be administered only by a healthcare professional.

Parenteral drug products should be inspected visually for foreign matter and discoloration prior to administration. It is important to shake the syringe vigorously for at least 15 seconds to ensure a homogeneous suspension. Inject INVEGA TRINZA within 5 minutes of shaking vigorously [see Dosage and Administration (2.8)] .

INVEGA TRINZA is intended for intramuscular use only. Do not administer by any other route. Avoid inadvertent injection into a blood vessel. Administer the dose in a single injection; do not administer the dose in divided injections. Inject slowly, deep into the deltoid or gluteal muscle.

INVEGA TRINZA must be administered using only the thin wall needles that are provided in the INVEGA TRINZA pack. Do not use needles from the 1-month paliperidone palmitate extended-release injectable suspension pack or other commercially-available needles to reduce the risk of blockage.

Deltoid Injection

The recommended needle size for administration of INVEGA TRINZA into the deltoid muscle is determined by the patient's weight:

- For patients weighing less than 90 kg, the 1-inch, 22 gauge thin wall needle is recommended.
- For patients weighing 90 kg or more, the 1½-inch, 22 gauge thin wall needle is recommended.

Administer into the center of the deltoid muscle. Deltoid injections should be alternated between the two deltoid muscles.

Gluteal Injection

Regardless of patient weight, the recommended needle size for administration of INVEGA TRINZA into the gluteal muscle is the 1½-inch, 22 gauge thin wall needle. Administer into the upper-outer quadrant of the gluteal muscle. Gluteal injections should be alternated between the two gluteal muscles.

Incomplete Administration

To avoid an incomplete administration of INVEGA TRINZA, ensure that the prefilled syringe is shaken vigorously for at least 15 seconds within 5 minutes prior to administration to ensure a homogeneous suspension and ensure the needle does not get clogged during injection [see Dosage and Administration (2.8)] .

However, in the event of an incompletely administered dose, do not re-inject the dose remaining in the syringe and do not administer another dose of INVEGA TRINZA. Closely monitor and treat the patient with oral supplementation as clinically appropriate until the next scheduled 3-month injection of INVEGA TRINZA.

2.2 Schizophrenia

Adults

INVEGA TRINZA is to be used only after INVEGA SUSTENNA (1-month paliperidone palmitate extended-release injectable suspension) has been established as adequate treatment for at least four months. In order to establish a consistent maintenance dose, it is recommended that the last two doses of INVEGA SUSTENNA be the same dosage strength before starting INVEGA TRINZA.

Initiate INVEGA TRINZA when the next 1-month paliperidone palmitate dose is scheduled with an INVEGA TRINZA dose based on the previous 1-month injection dose, using the equivalent 3.5-fold higher dose as shown in Table 1. INVEGA TRINZA may be administered up to 7 days before or after the monthly time point of the next scheduled paliperidone palmitate 1-month dose.

Table 1. INVEGA TRINZA Doses for Adult Patients Adequately Treated with INVEGA SUSTENNA
If the Last Dose of INVEGA SUSTENNA is: | Initiate INVEGA TRINZA at the Following Dose:
78 mg | 273 mg
117 mg | 410 mg
156 mg | 546 mg
234 mg | 819 mg
Conversion from the INVEGA SUSTENNA 39 mg dose was not studied.

Following the initial INVEGA TRINZA dose, INVEGA TRINZA should be administered every 3 months. If needed, dose adjustment can be made every 3 months in increments within the range of 273 mg to 819 mg based on individual patient tolerability and/or efficacy. Due to the long-acting nature of INVEGA TRINZA, the patient's response to an adjusted dose may not be apparent for several months [see Clinical Pharmacology (12.3)] .

2.3 Missed Doses

Dosing Window

Missing doses of INVEGA TRINZA should be avoided. If necessary, patients may be given the injection up to 2 weeks before or after the 3-month time point.

Missed Dose 3½ Months to 4 Months Since Last Injection

If more than 3½ months (up to but less than 4 months) have elapsed since the last injection of INVEGA TRINZA, the previously administered INVEGA TRINZA dose should be administered as soon as possible, then continue with the 3-month injections following this dose.

Missed Dose 4 Months to 9 Months Since Last Injection

If 4 months up to and including 9 months have elapsed since the last injection of INVEGA TRINZA, do NOT administer the next dose of INVEGA TRINZA. Instead, use the re-initiation regimen shown in Table 2.

Table 2. Re-initiation Regimen After Missing 4 Months to 9 Months of INVEGA TRINZA
If the Last Dose of INVEGA TRINZA was: | Administer INVEGA SUSTENNA, two doses one week apart (into deltoid muscle) |  | Then administer INVEGA TRINZA (into deltoid [See Instructions for Use for deltoid injection needle selection based on body weight.] or gluteal muscle)
If the Last Dose of INVEGA TRINZA was: | Day 1 | Day 8 | 1 month after Day 8
273 mg | 78 mg | 78 mg | 273 mg
410 mg | 117 mg | 117 mg | 410 mg
546 mg | 156 mg | 156 mg | 546 mg
819 mg | 156 mg | 156 mg | 819 mg

Missed Dose Longer than 9 Months Since Last Injection

If more than 9 months have elapsed since the last injection of INVEGA TRINZA, re-initiate treatment with the 1-month paliperidone palmitate extended-release injectable suspension as described in the prescribing information for that product. INVEGA TRINZA can then be resumed after the patient has been adequately treated with the 1-month paliperidone palmitate extended-release injectable suspension for at least 4 months.

2.4 Use with Risperidone or with Oral Paliperidone

Since paliperidone is the major active metabolite of risperidone, caution should be exercised when INVEGA TRINZA is coadministered with risperidone or oral paliperidone for extended periods of time. Safety data involving concomitant use of INVEGA TRINZA with other antipsychotics is limited.

2.5 Dosage Recommendations in Patients with Renal Impairment

INVEGA TRINZA has not been systematically studied in patients with renal impairment [see Clinical Pharmacology (12.3)] . For patients with mild renal impairment (creatinine clearance ≥ 50 mL/min to < 80 mL/min [Cockcroft-Gault Formula]), adjust dosage and stabilize the patient using the 1-month paliperidone palmitate extended-release injectable suspension, then transition to INVEGA TRINZA (see Table 1) [see Use in Specific Populations (8.6)and Clinical Pharmacology (12.3)]. Refer to the Prescribing Information of the 1-month paliperidone palmitate extended-release injectable suspension product for the recommended dosage in patients with mild renal impairment.

INVEGA TRINZA is not recommended in patients with moderate or severe renal impairment (creatinine clearance < 50 mL/min) [see Use in Specific Populations (8.6)and Clinical Pharmacology (12.3)] .

2.6 Switching from INVEGA TRINZA to the 1-Month Paliperidone Palmitate Extended-Release Injectable Suspension

For switching from INVEGA TRINZA to INVEGA SUSTENNA (1-month paliperidone palmitate extended-release injectable suspension), the 1-month paliperidone palmitate extended-release injectable suspension should be started 3 months after the last INVEGA TRINZA dose, using the equivalent 3.5-fold lower dose as shown in Table 3. The 1-month paliperidone palmitate extended-release injectable suspension should then continue, dosed at monthly intervals.

Table 3. Conversion from INVEGA TRINZA to INVEGA SUSTENNA
If the Last Dose of INVEGA TRINZA is: | Initiate [The initiation dosing as described in the prescribing information for INVEGA SUSTENNA is not required.] INVEGA SUSTENNA 3 Months Later at the Following Dose:
273 mg | 78 mg
410 mg | 117 mg
546 mg | 156 mg
819 mg | 234 mg

2.7 Switching from INVEGA TRINZA to Oral Paliperidone Extended-Release Tablets

For switching from INVEGA TRINZA to oral paliperidone extended-release tablets, the daily dosing of the paliperidone extended-release tablets should be started 3 months after the last INVEGA TRINZA dose and transitioned over the next several months following the last INVEGA TRINZA dose as described in Table 4. Table 4 provides dose conversion regimens to allow patients previously stabilized on different doses of INVEGA TRINZA to attain similar paliperidone exposure with once daily paliperidone extended-release tablets.

Table 4. INVEGA TRINZA Doses and Once-Daily Paliperidone Extended-Release Conversion Regimens Needed to Attain Similar Paliperidone Exposures
 | Weeks Since Last INVEGA TRINZA Dose
 | 3 months to 18 weeks | Longer than 18 weeks to 24 weeks | Longer than 24 weeks
Last INVEGA TRINZA Dose | Doses of oral paliperidone extended-release tablets
273 mg | 3 mg | 3 mg | 3 mg
410 mg | 3 mg | 3 mg | 6 mg
546 mg | 3 mg | 6 mg | 9 mg
819 mg | 6 mg | 9 mg | 12 mg

2.8 Instructions for Preparation and Administration

Administer every 3 months

Shake syringe vigorously for at least 15 seconds

For intramuscular injection only. Do not administer by any other route.

Important

INVEGA TRINZA should be administered by a healthcare professional as a single injection. DO NOT divide dose into multiple injections.

INVEGA TRINZA is intended for intramuscular use only. Inject slowly, deep into the muscle taking care to avoid injection into a blood vessel.

Read complete instructions prior to use.

Dosing

This medication should be administered once every 3 months.

Preparation

Peel off tab label from the syringe and place in patient record.

INVEGA TRINZA requires longer and more vigorous shaking than INVEGA SUSTENNA (1-month paliperidone palmitate extended-release injectable suspension). Shake the syringe vigorously, with the syringe tip pointing up, for at least 15 seconds within 5 minutes prior to administration (see Step 2).

Thin Wall Safety Needle Selection

Thin wall safety needles are designed to be used with INVEGA TRINZA. Therefore, it is important to only use the needles provided in the INVEGA TRINZAkit.

Dose pack contents

Prefilled Syringe

Thin Wall Safety Needles

1 Select needle

Needle selection is determined by injection area and patient weight.

If administering a Deltoid injection
If patient weighs:
Less than 90 kg
pink hub

If administering a Gluteal injection
If patient weighs:
Less than 90 kg
yellow hub

90 kg or more
yellow hub

90 kg or more
yellow hub

2 Prepare for injection

Check suspension

After shaking the syringe for at least 15 seconds, check the liquid in the viewing window.

The suspension should appear uniform and milky white in color.

It is also normal to see small air bubbles.

Open needle pouch and remove cap

First, open needle pouch by peeling the cover back half way. Place on a clean surface.

Then, holding the syringe upright, twist and pull the rubber cap to remove.

Grasp needle pouch

Fold back needle cover and plastic tray. Then, firmly grasp the needle sheath through the pouch, as shown.

Attach needle

Hold the syringe pointing up. Attach the safety needle to the syringe using a gentle twisting motion to avoid needle hub cracks or damage. Always check for signs of damage or leakage prior to administration.

Remove needle sheath

Pull the needle sheath away from the needle in a straight motion.

Do not twist the sheath, as this may loosen the needle from the syringe.

Remove air bubbles

Hold the syringe upright and tap gently to make any air bubbles rise to the top.

Remove air by pressing the plunger rod upward carefully until a drop of liquid comes out of the needle tip.

3 Inject

Inject dose

Slowly inject the entire contents of the syringe intramuscularly, deep into the selected deltoid or gluteal muscle.

Do not administer by any other route.

4 After injection

Secure needle

After the injection is complete, use your thumb or a flat surface to secure the needle in the safety device. The needle is secure when a "click" sound is heard.

Dispose properly

Dispose of the syringe and unused needle in an approved sharps container.

3 DOSAGE FORMS AND STRENGTHS

INVEGA TRINZA is available as a white to off-white aqueous extended-release injectable suspension for intramuscular injection in dose strengths of 273 mg/0.88 mL, 410 mg/1.32 mL, 546 mg/1.75 mL, and 819 mg/2.63 mL paliperidone palmitate in single-dose prefilled syringes.

4 CONTRAINDICATIONS

INVEGA TRINZA is contraindicated in patients with a known hypersensitivity to either paliperidone or risperidone, or to any of the excipients in the INVEGA TRINZA formulation. Hypersensitivity reactions, including anaphylactic reactions and angioedema, have been reported in patients treated with risperidone and in patients treated with paliperidone. Paliperidone palmitate is converted to paliperidone, which is a metabolite of risperidone.

5 WARNINGS AND PRECAUTIONS

5.1 Increased Mortality in Elderly Patients with Dementia-Related Psychosis

Elderly patients with dementia-related psychosis treated with antipsychotic drugs are at an increased risk of death. Analyses of 17 placebo-controlled trials (modal duration of 10 weeks), largely in patients taking atypical antipsychotic drugs, revealed a risk of death in drug-treated patients of between 1.6 to 1.7 times the risk of death in placebo-treated patients. Over the course of a typical 10-week controlled trial, the rate of death in drug-treated patients was about 4.5%, compared to a rate of about 2.6% in the placebo group. Although the causes of death were varied, most of the deaths appeared to be either cardiovascular (e.g., heart failure, sudden death) or infectious (e.g., pneumonia) in nature. Observational studies suggest that, similar to atypical antipsychotic drugs, treatment with conventional antipsychotic drugs may increase mortality. The extent to which the findings of increased mortality in observational studies may be attributed to the antipsychotic drug as opposed to some characteristic(s) of the patients is not clear. INVEGA TRINZA is not approved for the treatment of patients with dementia-related psychosis [see Boxed Warning and Warnings and Precautions (5.2)] .

5.2 Cerebrovascular Adverse Reactions, Including Stroke, in Elderly Patients with Dementia-Related Psychosis

In placebo-controlled trials with risperidone, aripiprazole, and olanzapine in elderly subjects with dementia, there was a higher incidence of cerebrovascular adverse reactions (cerebrovascular accidents and transient ischemic attacks) including fatalities compared to placebo-treated subjects. No studies have been conducted with oral paliperidone, the 1-month paliperidone palmitate extended-release injectable suspension, or INVEGA TRINZA in elderly patients with dementia. These medications are not approved for the treatment of patients with dementia-related psychosis [see Boxed Warning and Warnings and Precautions (5.1)] .

5.3 Neuroleptic Malignant Syndrome

Neuroleptic Malignant Syndrome (NMS), a potentially fatal symptom complex, has been reported in association with antipsychotic drugs, including paliperidone.

Clinical manifestations of NMS are hyperpyrexia, muscle rigidity, altered mental status including delirium, and autonomic instability (irregular pulse or blood pressure, tachycardia, diaphoresis, and cardiac dysrhythmia). Additional signs may include elevated creatine phosphokinase, myoglobinuria (rhabdomyolysis), and acute renal failure.

If NMS is suspected, immediately discontinue INVEGA TRINZA and provide symptomatic treatment and monitoring.

5.4 QT Prolongation

Paliperidone causes a modest increase in the corrected QT (QTc) interval. The use of paliperidone should be avoided in combination with other drugs that are known to prolong QTc including Class 1A (e.g., quinidine, procainamide) or Class III (e.g., amiodarone, sotalol) antiarrhythmic medications, antipsychotic medications (e.g., chlorpromazine, thioridazine), antibiotics (e.g., gatifloxacin, moxifloxacin), or any other class of medications known to prolong the QTc interval. Paliperidone should also be avoided in patients with congenital long QT syndrome and in patients with a history of cardiac arrhythmias.

Certain circumstances may increase the risk of the occurrence of Torsades de pointes and/or sudden death in association with the use of drugs that prolong the QTc interval, including (1) bradycardia; (2) hypokalemia or hypomagnesemia; (3) concomitant use of other drugs that prolong the QTc interval; and (4) presence of congenital prolongation of the QT interval.

The effects of paliperidone on the QT interval were evaluated in a double-blind, active-controlled (moxifloxacin 400 mg single dose), multicenter Thorough QT study with oral paliperidone in adult patients, and in four fixed-dose efficacy studies and one maintenance study of the 1-month paliperidone palmitate injectable product.

In the Thorough QT study (n=141), the 8 mg dose of immediate-release oral paliperidone (n=50) showed a mean placebo-subtracted increase from baseline in QTcLD (QT interval corrected for heart rate using the population specified linear derived method) of 12.3 msec (90% CI: 8.9; 15.6) on day 8 at 1.5 hours post-dose. The mean steady-state peak plasma concentration for this 8 mg dose of paliperidone immediate release (Cmax ss=113 ng/mL) was approximately 2-fold the exposure with the maximum recommended 819 mg dose of INVEGA TRINZA administered in the deltoid muscle (predicted median Cmax ss=56 ng/mL). In this same study, a 4 mg dose of the immediate-release oral formulation of paliperidone, for which Cmax ss=35 ng/mL, showed an increased placebo-subtracted QTcLD of 6.8 msec (90% CI: 3.6; 10.1) on day 2 at 1.5 hours post-dose.

In the four fixed-dose efficacy studies of the 1-month paliperidone palmitate injectable product, no subject had a change in QTcLD exceeding 60 msec and no subject had a QTcLD value of > 500 msec at any time point. In the maintenance study, no subject had a QTcLD change > 60 msec, and one subject had a QTcLD value of 507 msec (Bazett's QT corrected interval [QTcB] value of 483 msec); this latter subject also had a heart rate of 45 beats per minute.

In the long-term maintenance trial of INVEGA TRINZA in subjects with schizophrenia, an increase in QTcLD exceeding 60 msec was observed in 1 subject (< 1%) in the open-label phase, no subject had an increase in QTcLD exceeding 60 msec after treatment with INVEGA TRINZA in the double-blind phase, and no subject had a QTcLD value of > 480 msec at any point in the study.

5.5 Tardive Dyskinesia

Tardive dyskinesia, a syndrome consisting of potentially irreversible, involuntary, dyskinetic movements, may develop in patients treated with antipsychotic drugs. Although the prevalence of the syndrome appears to be highest among the elderly, especially elderly women, it is impossible to predict which patients will develop the syndrome. Whether antipsychotic drug products differ in their potential to cause tardive dyskinesia is unknown.

The risk of developing tardive dyskinesia and the likelihood that it will become irreversible appear to increase with the duration of treatment and the cumulative dose. The syndrome can develop after relatively brief treatment periods, even at low doses. It may also occur after discontinuation of treatment.

Tardive dyskinesia may remit, partially or completely, if antipsychotic treatment is discontinued. Antipsychotic treatment, itself, however, may suppress (or partially suppress) the signs and symptoms of the syndrome possibly masking the underlying process. The effect that symptomatic suppression has upon the long-term course of the syndrome is unknown.

Given these considerations, INVEGA TRINZA should be prescribed in a manner that is most likely to minimize the occurrence of tardive dyskinesia. Chronic antipsychotic treatment should generally be reserved for patients: (1) who suffer from a chronic illness that is known to respond to antipsychotic drugs, and (2) for whom alternative, equally effective, but potentially less harmful treatments are not available or appropriate. In patients who do require chronic treatment, use the lowest dose and the shortest duration of treatment producing a satisfactory clinical response. Periodically reassess the need for continued treatment.

If signs and symptoms of tardive dyskinesia appear in a patient treated with INVEGA TRINZA, drug discontinuation should be considered. Consideration should be given to the long-acting nature of INVEGA TRINZA. However, some patients may require treatment with INVEGA TRINZA despite the presence of the syndrome.

5.6 Metabolic Changes

Atypical antipsychotic drugs have been associated with metabolic changes that may increase cardiovascular/cerebrovascular risk. These metabolic changes include hyperglycemia, dyslipidemia, and body weight gain. While all of the drugs in the class have been shown to produce some metabolic changes, each drug has its own specific risk profile.

Hyperglycemia and Diabetes Mellitus

Hyperglycemia and diabetes mellitus, in some cases extreme and associated with ketoacidosis or hyperosmolar coma or death, have been reported in patients treated with all atypical antipsychotics. These cases were, for the most part, seen in post-marketing clinical use and epidemiologic studies, not in clinical trials. Hyperglycemia and diabetes have been reported in trial subjects treated with INVEGA TRINZA. Assessment of the relationship between atypical antipsychotic use and glucose abnormalities is complicated by the possibility of an increased background risk of diabetes mellitus in patients with schizophrenia and the increasing incidence of diabetes mellitus in the general population. Given these confounders, the relationship between atypical antipsychotic use and hyperglycemia-related adverse events is not completely understood. However, epidemiological studies suggest an increased risk of hyperglycemia-related adverse reactions in patients treated with the atypical antipsychotics.

Patients with an established diagnosis of diabetes mellitus who are started on atypical antipsychotics should be monitored regularly for worsening of glucose control. Patients with risk factors for diabetes mellitus (e.g., obesity, family history of diabetes) who are starting treatment with atypical antipsychotics should undergo fasting blood glucose testing at the beginning of treatment and periodically during treatment. Any patient treated with atypical antipsychotics should be monitored for symptoms of hyperglycemia including polydipsia, polyuria, polyphagia, and weakness. Patients who develop symptoms of hyperglycemia during treatment with atypical antipsychotics should undergo fasting blood glucose testing. In some cases, hyperglycemia has resolved when the atypical antipsychotic was discontinued; however, some patients required continuation of anti-diabetic treatment despite discontinuation of the suspect drug.

Data from the long-term maintenance trial with INVEGA TRINZA in subjects with schizophrenia are presented in Table 5.

Table 5. Change in Fasting Glucose from the Long-Term Maintenance Trial with INVEGA TRINZA in Subjects with Schizophrenia
 | Open-Label Phase (relative to open-label baseline) | Double-Blind Phase (relative to double-blind baseline)
 | Paliperidone Palmitate [During the open-label phase, subjects received several doses of the 1-month paliperidone palmitate extended-release injectable suspension followed by a single dose of INVEGA TRINZA [see Clinical Studies (14)] .] | Placebo | INVEGA TRINZA
 | Mean change from baseline (mg/dL)
 | n=397 | n=120 | n=138
Serum Glucose Change from baseline | 1.2 | -1.6 | -1.2
 | Proportion of Patients with Shifts
 | n=397 | n=128 | n=148
Serum Glucose Normal to High | 2.3% | 2.3% | 4.1%
(<100 mg/dL to ≥126 mg/dL) | (9/397) | (3/128) | (6/148)

Dyslipidemia

Undesirable alterations in lipids have been observed in patients treated with atypical antipsychotics.

Data from the long-term maintenance trial with INVEGA TRINZA in subjects with schizophrenia are presented in Table 6.

Table 6. Change in Fasting Lipids from the Long-Term Maintenance Trial with INVEGA TRINZA in Subjects with Schizophrenia
 | Open-Label Phase (relative to open-label baseline) | Double-Blind Phase (relative to double-blind baseline)
 | Paliperidone Palmitate [During the open-label phase, subjects received several doses of the 1-month paliperidone palmitate extended-release injectable suspension followed by a single dose of INVEGA TRINZA [see Clinical Studies (14)] .] | Placebo | INVEGA TRINZA
 | Mean change from baseline (mg/dL)
Cholesterol | n=400 | n=120 | n=138
Change from baseline | 0.5 | -0.4 | 0.9
LDL | n=396 | n=119 | n=138
Change from baseline | 1.1 | -0.4 | 1.1
HDL | n=397 | n=119 | n=138
Change from baseline | -0.2 | -0.5 | -1.3
Triglycerides | n=400 | n=120 | n=138
Change from baseline | 0.1 | -2.0 | 5.1
 | Proportion of Patients with Shifts
Cholesterol Normal to High | 2.0% | 3.9% | 1.4%
(<200 mg/dL to ≥240 mg/dL) | (8/400) | (5/128) | (2/148)
LDL Normal to High | 0.3% | 0.8% | 0%
(<100 mg/dL to ≥160 mg/dL) | (1/396) | (1/127) | (0/148)
HDL Normal to Low | 8.6% | 9.4% | 13.5%
(≥40 mg/dL to <40 mg/dL) | (34/397) | (12/127) | (20/148)
Triglycerides Normal to High | 4.5% | 1.6% | 8.1%
(<150 mg/dL to ≥200 mg/dL) | (18/400) | (2/128) | (12/148)

Weight Gain

Weight gain has been observed with atypical antipsychotic use. Clinical monitoring of weight is recommended.

Data on mean changes in body weight and the proportion of subjects meeting a weight gain criterion of ≥ 7% of body weight from the long-term maintenance trial with INVEGA TRINZA in subjects with schizophrenia are presented in Table 7.

Table 7. Change in Body Weight (kg) and the Proportion of Subjects with ≥ 7% Gain in Body Weight from the Long-Term Maintenance Trial with INVEGA TRINZA in Subjects with Schizophrenia
 | Open-Label Phase (relative to open-label baseline) | Double-Blind Phase (relative to double-blind baseline)
 | Paliperidone Palmitate [During the open-label phase, subjects received several doses of the 1-month paliperidone palmitate extended-release injectable suspension followed by a single dose of INVEGA TRINZA [see Clinical Studies (14)] .] | Placebo | INVEGA TRINZA
 | n=466 | n=142 | n=157
Weight (kg) Change from baseline | 1.42 | -1.28 | 0.94
Weight Gain ≥ 7% increase from baseline | 15.2% | 0.7% | 9.6%

5.7 Orthostatic Hypotension and Syncope

Paliperidone can induce orthostatic hypotension and syncope in some patients because of its alpha-adrenergic blocking activity. In the long-term maintenance trial, syncope was reported in < 1% (1/506) of subjects treated with the 1-month paliperidone palmitate extended-release injectable suspension during the open-label phase; there were no cases reported during the double-blind phase in either treatment group. In the long-term maintenance trial, orthostatic hypotension was reported as an adverse event by < 1% (1/506) of subjects treated with the 1-month paliperidone palmitate extended-release injectable suspension and < 1% (1/379) of subjects after receiving a single-dose of INVEGA TRINZA during the open-label phase; there were no cases reported during the double-blind phase in either treatment group.

INVEGA TRINZA should be used with caution in patients with known cardiovascular disease (e.g., heart failure, history of myocardial infarction or ischemia, conduction abnormalities), cerebrovascular disease, or conditions that predispose the patient to hypotension (e.g., dehydration, hypovolemia, and treatment with antihypertensive medications). Monitoring of orthostatic vital signs should be considered in patients who are vulnerable to hypotension.

5.8 Falls

Somnolence, postural hypotension, motor and sensory instability have been reported with the use of antipsychotics, including INVEGA TRINZA, which may lead to falls and, consequently, fractures or other fall-related injuries. For patients, particularly the elderly, with diseases, conditions, or medications that could exacerbate these effects, assess the risk of falls when initiating antipsychotic treatment and recurrently for patients on long-term antipsychotic therapy.

5.9 Leukopenia, Neutropenia, and Agranulocytosis

In clinical trial and/or postmarketing experience, events of leukopenia and neutropenia have been reported temporally related to antipsychotic agents, including INVEGA TRINZA. Agranulocytosis has also been reported.

Possible risk factors for leukopenia/neutropenia include pre-existing low white blood cell count (WBC)/absolute neutrophil count (ANC) and history of drug-induced leukopenia/neutropenia. In patients with a history of a clinically significant low WBC/ANC or a drug-induced leukopenia/neutropenia, perform a complete blood count (CBC) frequently during the first few months of therapy. In such patients, consider discontinuation of INVEGA TRINZA at the first sign of a clinically significant decline in WBC in the absence of other causative factors.

Monitor patients with clinically significant neutropenia for fever or other symptoms or signs of infection and treated promptly if such symptoms or signs occur. Discontinue INVEGA TRINZA in patients with severe neutropenia (absolute neutrophil count <1000/mm^3) and follow their WBC until recovery.

5.10 Hyperprolactinemia

Like other drugs that antagonize dopamine D2 receptors, paliperidone elevates prolactin levels and the elevation persists during chronic administration. Paliperidone has a prolactin-elevating effect similar to that seen with risperidone, a drug that is associated with higher levels of prolactin than other antipsychotic drugs.

Hyperprolactinemia, regardless of etiology, may suppress hypothalamic GnRH, resulting in reduced pituitary gonadotrophin secretion. This, in turn, may inhibit reproductive function by impairing gonadal steroidogenesis in both female and male patients. Galactorrhea, amenorrhea, gynecomastia, and impotence have been reported in patients receiving prolactin-elevating compounds. Long-standing hyperprolactinemia when associated with hypogonadism may lead to decreased bone density in both female and male subjects.

Tissue culture experiments indicate that approximately one-third of human breast cancers are prolactin dependent in vitro, a factor of potential importance if the prescription of these drugs is considered in a patient with previously detected breast cancer. An increase in the incidence of pituitary gland, mammary gland, and pancreatic islet cell neoplasia (mammary adenocarcinomas, pituitary and pancreatic adenomas) was observed in the risperidone carcinogenicity studies conducted in mice and rats [see Nonclinical Toxicology (13.1)] . Published epidemiologic studies have shown inconsistent results when exploring the potential association between hyperprolactinemia and breast cancer.

In a long-term maintenance trial of INVEGA TRINZA, elevations of prolactin to above the reference range (>13.13 ng/mL in males and >26.72 ng/mL in females) relative to open-label baseline at any time during the double-blind phase were noted in a higher percentage of males in the INVEGA TRINZA group than in the placebo group (46% vs. 25%) and in a higher percentage of females in the INVEGA TRINZA group than in the placebo group (32% vs. 15%). During the double-blind phase, 1 female (2.4%) in the INVEGA TRINZA group experienced an adverse reaction of amenorrhea, while no potentially prolactin-related adverse reactions were noted among females in the placebo group. There were no potentially prolactin-related adverse reactions among males in either group.

Prior to the double-blind phase (during the 29-week open-label phase of the long-term maintenance trial), the mean (SD) serum prolactin values at baseline in males (N=368) were 17.1 (13.55) ng/mL and 51.6 (40.85) ng/mL in females (N=122). Twelve weeks after a single injection of INVEGA TRINZA at the end of the open-label phase, mean (SD) prolactin values were 25.8 (13.49) ng/mL in males (N=322) and 70.6 (40.23) ng/mL in females (N=107). During the open-label phases 27% of females and 42% of males experienced elevations of prolactin above the reference range relative to baseline, and a higher proportion of females experienced potentially prolactin-related adverse reactions compared to males (7.9% vs. 3.7%). Amenorrhea (4.7%) and galactorrhea (3.1%) were the most commonly observed (≥3%) potentially prolactin-related adverse reactions in females. Among males in the open-label phase, no potentially prolactin-related adverse reaction was observed with a rate greater than 3%.

5.11 Potential for Cognitive and Motor Impairment

Somnolence, sedation, and dizziness were reported as adverse reactions in subjects treated with INVEGA TRINZA [see Adverse Reactions (6.1)] . Antipsychotics, including INVEGA TRINZA, have the potential to impair judgment, thinking, or motor skills. Patients should be cautioned about performing activities requiring mental alertness, such as operating hazardous machinery or operating a motor vehicle, until they are reasonably certain that paliperidone therapy does not adversely affect them.

5.12 Seizures

In the long-term maintenance trial there were no reports of seizures or convulsions. In the pivotal clinical studies with the 1-month paliperidone palmitate extended-release injectable suspension which included four fixed-dose, double-blind, placebo-controlled studies in subjects with schizophrenia, <1% (1/1293) of subjects treated with the 1-month injection experienced an adverse event of convulsion compared with <1% (1/510) of placebo-treated subjects who experienced an adverse event of grand mal convulsion.

Like other antipsychotic drugs, INVEGA TRINZA should be used cautiously in patients with a history of seizures or other conditions that potentially lower the seizure threshold. Conditions that lower the seizure threshold may be more prevalent in patients 65 years or older.

5.13 Dysphagia

Esophageal dysmotility and aspiration have been associated with antipsychotic drug use. INVEGA TRINZA and other antipsychotic drugs should be used cautiously in patients at risk for aspiration pneumonia.

5.14 Priapism

Drugs with alpha-adrenergic blocking effects have been reported to induce priapism. Although no cases of priapism have been reported in clinical trials with INVEGA TRINZA, priapism has been reported with oral paliperidone during postmarketing surveillance. Severe priapism may require surgical intervention.

5.15 Disruption of Body Temperature Regulation

Disruption of the body's ability to reduce core body temperature has been attributed to antipsychotic agents. Appropriate care is advised when prescribing INVEGA TRINZA to patients who will be experiencing conditions which may contribute to an elevation in core body temperature, e.g., exercising strenuously, exposure to extreme heat, receiving concomitant medication with anticholinergic activity, or being subject to dehydration.

6 ADVERSE REACTIONS

The following are discussed in more detail in other sections of the labeling:

- Increased mortality in elderly patients with dementia-related psychosis [see Boxed Warning and Warnings and Precautions (5.1)]
- Cerebrovascular adverse reactions, including stroke, in elderly patients with dementia-related psychosis [see Warnings and Precautions (5.2)]
- Neuroleptic malignant syndrome [see Warnings and Precautions (5.3)]
- QT prolongation [see Warnings and Precautions (5.4)]
- Tardive dyskinesia [see Warnings and Precautions (5.5)]
- Metabolic changes [see Warnings and Precautions (5.6)]
- Orthostatic hypotension and syncope [see Warnings and Precautions (5.7)]
- Falls [see Warnings and Precautions (5.8)]
- Leukopenia, neutropenia, and agranulocytosis [see Warnings and Precautions (5.9)]
- Hyperprolactinemia [see Warnings and Precautions (5.10)]
- Potential for cognitive and motor impairment [see Warnings and Precautions (5.11)]
- Seizures [see Warnings and Precautions (5.12)]
- Dysphagia [see Warnings and Precautions (5.13)]
- Priapism [see Warnings and Precautions (5.14)]
- Disruption of body temperature regulation [see Warnings and Precautions (5.15)]

6.1 Clinical Trials Experience

Because clinical trials are conducted under widely varying conditions, adverse reaction rates observed in the clinical trials of a drug cannot be directly compared to rates in the clinical trials of another drug and may not reflect the rates observed in clinical practice.

Patient Exposure

The data described in this section include data from two clinical trials. One is a long-term maintenance trial, in which 506 subjects with schizophrenia received several doses of the 1-month paliperidone palmitate extended-release injectable suspension during the open-label phase, of which 379 subjects continued to receive a single injection of INVEGA TRINZA during the open-label phase, and 160 subjects were subsequently randomized to receive at least one dose of INVEGA TRINZA and 145 subjects received placebo during the double-blind placebo-controlled phase. The mean (SD) duration of exposure during the double-blind phase was 150 (79) days in the placebo group and 175 (90) days in the INVEGA TRINZA group. The other is a Phase 1 study (N=308), which included patients with schizophrenia who received a single injection of INVEGA TRINZA concomitantly with other oral antipsychotics.

Adverse Reactions in a Double-Blind, Placebo-Controlled (Long-Term Maintenance) Clinical Trial

Commonly Observed Adverse Reactions: The most common adverse reactions (incidence at least 5% in the open-label phase, or in the INVEGA TRINZA group and at least twice the incidence in the placebo group during the double-blind phase) were injection site reaction, weight increased, headache, upper respiratory tract infection, akathisia, and parkinsonism.

Discontinuation of Treatment Due to Adverse Events: The percentages of subjects who discontinued due to adverse events in the long-term maintenance trial were 5.1% during the open-label phase. During the double-blind phase, no INVEGA TRINZA-treated subject and one placebo-treated subject discontinued due to adverse events.

Adverse Reactions Occurring at an Incidence of 2% or More in INVEGA TRINZA- Treated Patients: The safety profile of INVEGA TRINZA was similar to that seen with the 1-month paliperidone extended-release injectable suspension. Table 8 lists the adverse reactions reported in a long-term maintenance trial in subjects with schizophrenia.

Table 8. Incidences of Adverse Reactions 2% or More of INVEGA TRINZA-Treated Patients (and Greater than Placebo) for the Open-Label and Double-Blind Phases of a Long-Term Maintenance Trial in Patients with Schizophrenia
 | --- Open Label----- | ------------ Double Blind -------------
 | Paliperidone Palmitate [During the open-label phase, subjects received several doses of the 1-month paliperidone palmitate extended-release injectable suspension followed by a single dose of INVEGA TRINZA prior to randomization to either placebo or INVEGA TRINZA in the subsequent double-blind phase [see Clinical Studies (14)] .] | Placebo | INVEGA TRINZA
System Organ Class | (N=506) | (N=145) | (N=160)
Adverse Reaction [The following terms were combined: Injection site reaction includes Injection site reaction, Injection site erythema, Injection site extravasation, Injection site induration, Injection site inflammation, Injection site mass, Injection site nodule, Injection site pain, Injection site swelling. Weight increased includes Weight increased, Waist circumference increased. Upper respiratory tract infection includes Upper respiratory tract infection, Nasopharyngitis, Pharyngitis, Rhinitis. Akathisia includes Akathisia, Restlessness. Parkinsonism includes Parkinsonism, Cogwheel rigidity, Drooling, Extrapyramidal disorder, Hypokinesia, Muscle rigidity, Muscle tightness, Musculoskeletal stiffness, Salivary hypersecretion.] | % [Incidence is based on the number of subjects experiencing at least one adverse event, not the number of events.] | % | %
General disorders and administration site conditions
Injection site reaction | 12 | 0 | 3
Infections and infestations
Upper respiratory tract infection | 5 | 4 | 10
Urinary tract infection | <1 | 1 | 3
Metabolism and nutrition disorders
Weight increased | 10 | 3 | 9
Nervous system disorders
Akathisia | 5 | 2 | 5
Headache | 7 | 4 | 9
Parkinsonism | 5 | 0 | 4
Table includes adverse reactions that were reported in 2% or more of subjects in the INVEGA TRINZA group during the double-blind phase and which occurred at greater incidence than in the placebo group.

Demographic Differences

An examination of population subgroups in the long-term maintenance trial did not reveal any evidence of differences in safety on the basis of age, gender, or race alone; however, there were few subjects 65 years of age and older.

Extrapyramidal Symptoms (EPS)

Data from the long-term maintenance trial provided information regarding EPS. Several methods were used to measure EPS: (1) the Simpson-Angus global score which broadly evaluates parkinsonism, (2) the Barnes Akathisia Rating Scale global clinical rating score which evaluates akathisia, (3) the Abnormal Involuntary Movement Scale scores which evaluates dyskinesia, and (4) use of anticholinergic medications to treat EPS (Table 9), and (5) incidence of spontaneous reports of EPS (Table 10).

Table 9. Extrapyramidal Symptoms (EPS) Assessed by Incidence of Rating Scales and Use of Anticholinergic Medication
 |  | Percentage of Subjects
 | Open-label Phase | Double-blind Phase
 | Paliperidone Palmitate [During the open-label phase, subjects received several doses of the 1-month paliperidone palmitate extended-release injectable suspension followed by a single dose of INVEGA TRINZA [see Clinical Studies (14)] .] | Placebo | INVEGA TRINZA
Scale | (N=506) % | (N=145) % | (N=160) %
Parkinsonism [For Parkinsonism, percent of subjects with Simpson-Angus Total score > 0.3 at any time (Global score defined as total sum of items score divided by the number of items)] | 6 | 3 | 6
Akathisia [For Akathisia, percent of subjects with Barnes Akathisia Rating Scale global score ≥ 2 at any time] | 3 | 1 | 4
Dyskinesia [For Dyskinesia, percent of subjects with a score ≥ 3 on any of the first 7 items or a score ≥ 2 on two or more of any of the first 7 items of the Abnormal Involuntary Movement Scale at any time] | 1 | 3 | 3
Use of Anticholinergic Medications [Percent of subjects who received anticholinergic medications to treat EPS] | 11 | 9 | 11

Table 10. Extrapyramidal Symptoms (EPS)-Related Events by MedDRA Preferred Term
 |  | Percentage of Subjects
 | Open-label Phase | Double-blind Phase
 | Paliperidone Palmitate [During the open-label phase, subjects received several doses of the 1-month paliperidone palmitate extended-release injectable suspension followed by a single dose of INVEGA TRINZA [see Clinical Studies (14)] .] | Placebo | INVEGA TRINZA
EPS Group | (N=506) % | (N=145) % | (N=160) %
Overall percentage of subjects with EPS-related adverse events | 10 | 3 | 8
Parkinsonism | 4 | 0 | 4
Hyperkinesia | 5 | 2 | 5
Tremor | 2 | 0 | 1
Dyskinesia | <1 | 1 | 1
Dystonia | 1 | 0 | 1
Parkinsonism group includes: Cogwheel rigidity, drooling, extrapyramidal disorder, hypokinesia, muscle rigidity, muscle tightness, musculoskeletal stiffness, parkinsonism
Hyperkinesia group includes: Akathisia, restlessness
Dystonia group includes: Blepharospasm, dystonia, muscle spasms

After injection of INVEGA TRINZA in the open-label phase, 12 (3.2%) subjects had EPS that were new or worsened in severity, with events under the groupings of hyperkinesia (1.6%) and parkinsonism (1.3%) being the most common. After injection of INVEGA TRINZA in the open-label or double-blind phases, one subject discontinued from the open-label phase due to restlessness.

An examination of the time to EPS during the double-blind phase showed no clustering of these events at visits that would be expected to correspond to median peak plasma concentrations of paliperidone for subjects randomized to INVEGA TRINZA.

Dystonia

Symptoms of dystonia, prolonged abnormal contractions of muscle groups, may occur in susceptible individuals during the first few days of treatment. Dystonic symptoms include: spasm of the neck muscles, sometimes progressing to tightness of the throat, swallowing difficulty, difficulty breathing, and/or protrusion of the tongue. While these symptoms can occur at low doses, they occur more frequently and with greater severity with high potency and at higher doses of first generation antipsychotic drugs. An elevated risk of acute dystonia is observed in males and younger age groups.

Pain Assessment and Local Injection Site Reactions

Investigator ratings of injection site.Redness and swelling were observed in 2% or less of subjects in the INVEGA TRINZA and placebo groups during the double-blind phase of the long-term maintenance study, and were rated mild based on investigator ratings using a 4-point scale (0=absent; 1=mild; 2=moderate; 3=severe). There were no reports of induration in either group during the double-blind phase, and no subjects discontinued due to INVEGA TRINZA injection.

Subject ratings of injection site pain.Subject evaluations of injection pain during the double-blind phase also were similar for placebo and INVEGA TRINZA.

Subject ratings of injection site pain in the single-dose Phase 1 study allowed for assessment of the temporal course of injection site pain. Residual injection pain peaked 1 or 6 hours after injection, and trended downward 3 days after the injection. Deltoid injections were numerically more painful than gluteal injections, although most pain ratings were below 10 mm on a 100-mm scale.

Other Adverse Reactions Observed During the Clinical Trial Evaluation of INVEGA TRINZA

The following additional adverse reactions were identified in the long-term maintenance trial. The following list does not include reactions: 1) already listed in previous tables or elsewhere in labeling, 2) for which a drug cause was remote, 3) which were so general as to be uninformative, 4) which were not considered to have significant clinical implications, or 5) occurred at an incidence lower than that of placebo-treated patients.

Cardiac disorders: tachycardia

Gastrointestinal disorders: nausea, vomiting

Metabolism and nutrition disorders: hyperinsulinemia

Psychiatric disorders: anxiety

Additional Adverse Reactions Reported in Clinical Trials with the 1-Month Paliperidone Palmitate Extended-Release Injectable Suspension

The following is a list of additional adverse reactions that have been reported in clinical trials with the 1-month paliperidone palmitate extended-release injectable suspension:

Cardiac disorders: atrioventricular block first degree, bradycardia, bundle branch block, palpitations, postural orthostatic tachycardia syndrome

Ear and labyrinth disorders: vertigo

Eye disorders: eye movement disorder, eye rolling, oculogyric crisis, vision blurred

Gastrointestinal disorders: abdominal discomfort/abdominal pain upper, diarrhea, dry mouth, toothache

General disorders and administration site conditions: asthenia, fatigue

Immune system disorders: hypersensitivity

Investigations:electrocardiogram abnormal

Metabolism and nutrition disorders: decreased appetite, increased appetite

Musculoskeletal and connective tissue disorders: back pain, myalgia, pain in extremity, joint stiffness, muscle spasms, muscle twitching, nuchal rigidity

Nervous system disorders: bradykinesia, cerebrovascular accident, convulsion, dizziness, dizziness postural, dysarthria, hypertonia, lethargy, oromandibular dystonia, psychomotor hyperactivity, syncope

Psychiatric disorders: agitation, nightmare

Reproductive system and breast disorders: breast discharge, erectile dysfunction, gynecomastia, menstrual disorder, menstruation delayed, menstruation irregular, sexual dysfunction

Respiratory, thoracic and mediastinal disorders: cough

Skin and subcutaneous tissue disorders: drug eruption, pruritus, pruritus generalized, rash, urticaria

Vascular disorders: hypertension

Additional Adverse Reactions Reported in Clinical Trials with Oral Paliperidone

The following is a list of additional adverse reactions that have been reported in clinical trials with oral paliperidone:

Cardiac disorders: bundle branch block left, sinus arrhythmia

Gastrointestinal disorders: abdominal pain, constipation, flatulence, small intestinal obstruction

General disorders and administration site conditions: edema, edema peripheral

Immune system disorders: anaphylactic reaction

Musculoskeletal and connective tissue disorders: arthralgia, musculoskeletal pain, torticollis, trismus

Nervous system disorders: grand mal convulsion, parkinsonian gait, transient ischemic attack

Psychiatric disorders:sleep disorder

Reproductive system and breast disorders: breast engorgement, breast tenderness/breast pain, retrograde ejaculation

Respiratory, thoracic and mediastinal disorders:nasal congestion, pharyngolaryngeal pain, pneumonia aspiration

Skin and subcutaneous tissue disorders:rash papular

Vascular disorders: hypotension, ischemia

6.2 Postmarketing Experience

The following adverse reactions have been identified during postapproval use of paliperidone; because these reactions were reported voluntarily from a population of uncertain size, it is not always possible to reliably estimate their frequency or establish a causal relationship to drug exposure: angioedema, catatonia, ileus, somnambulism, swollen tongue, thrombotic thrombocytopenic purpura, urinary incontinence, and urinary retention.

Cases of anaphylactic reaction after injection with the 1-month paliperidone palmitate extended-release suspension have been reported during postmarketing experience in patients who have previously tolerated oral risperidone or oral paliperidone.

Paliperidone is the major active metabolite of risperidone. Adverse reactions reported with oral risperidone and risperidone long-acting injection can be found in the Adverse Reactions (6)sections of the package inserts for those products.

7 DRUG INTERACTIONS

7.1 Drugs Having Clinically Important Interactions with INVEGA TRINZA

Because paliperidone palmitate is hydrolyzed to paliperidone [see Clinical Pharmacology (12.3)] , results from studies with oral paliperidone should be taken into consideration when assessing drug-drug interaction potential. In addition, consider the 3-month dosing interval and long half-life of INVEGA TRINZA [see Dosage and Administration (2.1)and Clinical Pharmacology (12.3)] .

Table 11. Clinically Important Drug Interactions with INVEGA TRINZA
Concomitant Drug Name or Drug Class | Clinical Rationale | Clinical Recommendation
Centrally Acting Drugs and Alcohol | Given the primary CNS effects of paliperidone, concomitant use of centrally acting drugs and alcohol may modulate the CNS effects of INVEGA TRINZA. | INVEGA TRINZA should be used with caution in combination with other centrally acting drugs and alcohol [see Adverse Reactions (6.1, 6.2)] .
Drugs with Potential for Inducing Orthostatic Hypotension | Because INVEGA TRINZA has the potential for inducing orthostatic hypotension, an additive effect may occur when INVEGA TRINZA is administered with other therapeutic agents that have this potential [see Warnings and Precautions (5.7)] . | Monitor orthostatic vital signs in patients who are vulnerable to hypotension [see Warnings and Precautions (5.7)] .
Strong Inducers of CYP3A4 and P-gp (e.g., carbamazepine, rifampin, or St. John's Wort) | The concomitant use of paliperidone and strong inducers of CYP3A4 and P-gp may decrease the exposure of paliperidone [see Clinical Pharmacology (12.3)] . | Avoid using CYP3A4 and/or P-gp inducers with INVEGA TRINZA during the 3-month dosing interval, if possible. If administering a strong inducer is necessary, consider managing the patient using paliperidone extended-release tablets [see Dosage and Administration (2.7)] .
Levodopa and Other Dopamine Agonists | Paliperidone may antagonize the effect of levodopa and other dopamine agonists. | Monitor and manage patient as clinically appropriate.

7.2 Drugs Having No Clinically Important Interactions with INVEGA TRINZA

Based on pharmacokinetic studies with oral paliperidone, no dosage adjustment of INVEGA TRINZA is required when administered concomitantly with valproate [see Clinical Pharmacology (12.3)]. Additionally, no dosage adjustment is necessary for valproate when co-administered with INVEGA TRINZA [see Clinical Pharmacology (12.3)] .

Pharmacokinetic interaction between lithium and INVEGA TRINZA is unlikely.

Paliperidone is not expected to cause clinically important pharmacokinetic interactions with drugs that are metabolized by cytochrome P450 isozymes. In vitro studies indicate that CYP2D6 and CYP3A4 may be involved in paliperidone metabolism; however, there is no evidence in vivo that inhibitors of these enzymes significantly affect the metabolism of paliperidone. Paliperidone is not a substrate of CYP1A2, CYP2A6, CYP2C9, and CYP2C19; an interaction with inhibitors or inducers of these isozymes is unlikely. [See Clinical Pharmacology (12.3)]

8 USE IN SPECIFIC POPULATIONS

8.1 Pregnancy

Pregnancy Exposure Registry

There is a pregnancy exposure registry that monitors pregnancy outcomes in women exposed to atypical antipsychotics, including INVEGA TRINZA, during pregnancy. Healthcare providers are encouraged to register patients by contacting the National Pregnancy Registry for Atypical Antipsychotics at 1-866-961-2388 or online at http://womensmentalhealth.org/clinical-and-research-programs/pregnancyregistry/.

Risk Summary

Neonates exposed to antipsychotic drugs during the third trimester of pregnancy are at risk for extrapyramidal and/or withdrawal symptoms following delivery (see Clinical Considerations) . Overall, available data from published epidemiologic studies of pregnant women exposed to paliperidone have not established a drug-associated risk for major birth defects, miscarriage, or adverse maternal or fetal outcomes (see Data) . There are risks to the mother associated with untreated schizophrenia and with exposure to antipsychotics, including INVEGA TRINZA during pregnancy (see Clinical Considerations) . Paliperidone has been detected in plasma in adult subjects up to 18 months after a single-dose administration of INVEGA TRINZA [see Clinical Pharmacology (12.3)] , and the clinical significance of INVEGA TRINZA administered before pregnancy or anytime during pregnancy is not known.

The estimated background risk of major birth defects and miscarriage for the indicated population is unknown. All pregnancies have a background risk of birth defects, loss, or other adverse outcomes. In the U.S. general population, the estimated background risk of major birth defects and miscarriage in clinically recognized pregnancies is 2–4% and 15–20%, respectively.

In animal reproduction studies, there were no treatment related effects on the offspring when pregnant rats were injected intramuscularly with paliperidone palmitate during the period of organogenesis at doses up to 10 times the maximum recommended human dose (MRHD) of 234 mg paliperidone based on mg/m^2body surface area. There were no increases in fetal abnormalities when pregnant rats and rabbits were treated orally with paliperidone during the period of organogenesis with up to 8 times the MRHD of 12 mg of paliperidone based on mg/m^2body surface area. Additional reproduction toxicity studies were conducted with orally administered risperidone, which is extensively converted to paliperidone (see Animal data).

Clinical Considerations

Disease-associated maternal and/or embryo/fetal risk

There is a risk to the mother from untreated schizophrenia, including increased risk of relapse, hospitalization, and suicide. Schizophrenia is associated with increased adverse perinatal outcomes, including preterm birth. It is not known if this is a direct result of the illness or other comorbid factors.

Fetal/Neonatal Adverse Reactions

Extrapyramidal and/or withdrawal symptoms, including agitation, hypertonia, hypotonia, tremor, somnolence, respiratory distress, and feeding disorder have been reported in neonates who were exposed to antipsychotic drugs, including INVEGA TRINZA, during the third trimester of pregnancy. These symptoms have varied in severity. Monitor neonates for extrapyramidal and/or withdrawal symptoms and manage symptoms appropriately. Some neonates recovered within hours or days without specific treatment; others required prolonged hospitalization.

Data

Human Data

Published data from observational studies, birth registries, and case reports on the use of atypical antipsychotics during pregnancy do not report a clear association with antipsychotics and major birth defects. A prospective observational study including 6 women treated with risperidone, the parent compound of paliperidone, demonstrated placental passage of risperidone and paliperidone. A retrospective cohort study from a Medicaid database of 9258 women exposed to antipsychotics during pregnancy did not indicate an overall increased risk for major birth defects. There was a small increase in the risk of major birth defects (RR=1.26, 95% CI 1.02–1.56) and of cardiac malformations (RR=1.26, 95% CI 0.88–1.81) in a subgroup of 1566 women exposed to the parent compound of paliperidone, risperidone, during the first trimester of pregnancy; however, there is no mechanism of action to explain the difference in malformation rates.

Animal Data

No developmental toxicity studies were conducted with the 3-month paliperidone palmitate extended-release injectable suspension.

There were no treatment-related effects on the offspring when pregnant rats were injected intramuscularly with 1-month paliperidone palmitate extended-release injectable suspension during the period of organogenesis at doses up to 250 mg/kg, which is 3 times the MRHD of 819 mg of the 3-month paliperidone palmitate extended-release injectable suspension based on mg/m^2body surface area.

In animal reproduction studies, there were no increases in fetal abnormalities when pregnant rats and rabbits were treated orally with paliperidone during the period of organogenesis with up to 8 times the MRHD of 12 mg based on mg/m^2body surface area.

Additional reproduction toxicity studies were conducted with orally administered risperidone, which is extensively converted to paliperidone. Cleft palate was observed in the offspring of pregnant mice treated with risperidone at 3 to 4 times the MRHD of 16 mg based on mg/m^2body surface area; maternal toxicity occurred at 4 times the MHRD. There was no evidence of teratogenicity in embryo-fetal developmental toxicity studies with risperidone in rats and rabbits at doses up to 6 times the MRHD of 16 mg/day risperidone based on mg/m^2body surface area. When the offspring of pregnant rats, treated with risperidone at 0.6 times the MRHD based on mg/m^2body surface area, reached adulthood, learning was impaired. Increased neuronal cell death occurred in the fetal brains of the offspring of pregnant rats treated at 0.5 to 1.2 times the MRHD; the postnatal development and growth of the offspring was delayed.

In rat reproduction studies with risperidone, pup deaths occurred at oral doses which are less than the MRHD of risperidone based on mg/m^2body surface area; it is not known whether these deaths were due to a direct effect on the fetuses or pups or, to effects on the dams (see RISPERDAL package insert).

8.2 Lactation

Risk Summary

Limited data from published literature report the presence of paliperidone in human breast milk. There is no information on the effects on the breastfed infant, or the effects on milk production; however, there are reports of sedation, failure to thrive, jitteriness, and extrapyramidal symptoms (tremors and abnormal muscle movements) in breastfed infants exposed to paliperidone's parent compound, risperidone (see Clinical Considerations) . Paliperidone has been detected in plasma in adult subjects up to 18 months after a single-dose administration of INVEGA TRINZA, and the clinical significance on the breastfed infant is not known [see Clinical Pharmacology (12.3)]. The developmental and health benefits of breastfeeding should be considered along with the mother's clinical need for INVEGA TRINZA and any potential adverse effects on the breastfed child from INVEGA TRINZA or from the mother's underlying condition.

Clinical Considerations

Infants exposed to INVEGA TRINZA through breastmilk should be monitored for excess sedation, failure to thrive, jitteriness, and extrapyramidal symptoms (tremors and abnormal muscle movements).

8.3 Females and Males of Reproductive Potential

Infertility

Females

Based on the pharmacologic action of paliperidone (D2 receptor antagonism), treatment with INVEGA TRINZA may result in an increase in serum prolactin levels, which may lead to a reversible reduction in fertility in females of reproductive potential [see Warnings and Precautions (5.10)].

8.4 Pediatric Use

Safety and effectiveness of INVEGA TRINZA in patients less than 18 years of age have not been established. Use of INVEGA TRINZA is not recommended in pediatric patients because of the potential longer duration of an adverse event compared to shorter-acting products. In clinical trials of oral paliperidone, there were notably higher incidences of dystonia, hyperkinesia, tremor, and parkinsonism in the adolescent population as compared to the adult studies.

Juvenile Animal Studies

No juvenile animal studies were conducted with the 3-month paliperidone palmitate extended-release injectable suspension.

In a study in which juvenile rats were treated with oral paliperidone from days 24 to 73 of age, a reversible impairment of performance in a test of learning and memory was seen, in females only, with a no-effect dose of 0.63 mg/kg/day, which produced plasma levels (AUC) of paliperidone similar to those in adolescents dosed at 12 mg/day. No other consistent effects on neurobehavioral or reproductive development were seen up to the highest dose tested (2.5 mg/kg/day), which produced plasma levels of paliperidone 2–3 times those in adolescents.

Juvenile dogs were treated for 40 weeks with oral risperidone, which is extensively metabolized to paliperidone in animals and humans, at doses of 0.31, 1.25, or 5 mg/kg/day. Decreased bone length and density were seen with a no-effect dose of 0.31 mg/kg/day, which produced plasma levels (AUC) of risperidone plus paliperidone which were similar to those in children and adolescents receiving the MRHD of risperidone. In addition, a delay in sexual maturation was seen at all doses in both males and females. The above effects showed little or no reversibility in females after a 12-week drug-free recovery period.

The long-term effects of INVEGA TRINZA on growth and sexual maturation have not been fully evaluated in children and adolescents.

8.5 Geriatric Use

Clinical studies of INVEGA TRINZA did not include sufficient numbers of subjects aged 65 and over to determine whether they respond differently from younger subjects. Other reported clinical experience has not identified differences in responses between the elderly and younger patients.

This drug is known to be substantially excreted by the kidney and clearance is decreased in patients with renal impairment [see Clinical Pharmacology (12.3)] , who should be given reduced doses. Because elderly patients are more likely to have decreased renal function, monitor renal function and adjust dosage [see Dosage and Administration (2.5)].

8.6 Renal Impairment

Use of INVEGA TRINZA is not recommended in patients with moderate or severe renal impairment (creatinine clearance < 50 mL/min). Use of INVEGA TRINZA in patients with mild renal impairment (creatinine clearance ≥ 50 mL/min to < 80 mL/min) is based on the previous dose of the 1-month paliperidone palmitate extended-release injectable suspension that the patient was stabilized on prior to initiation of INVEGA TRINZA [see Dosage and Administration (2.5)and Clinical Pharmacology (12.3)] .

8.7 Hepatic Impairment

INVEGA TRINZA has not been studied in patients with hepatic impairment. Based on a study with oral paliperidone, no dose adjustment is required in patients with mild or moderate hepatic impairment. Paliperidone has not been studied in patients with severe hepatic impairment [see Clinical Pharmacology (12.3)] .

8.8 Patients with Parkinson's Disease or Lewy Body Dementia

Patients with Parkinson's Disease or Dementia with Lewy Bodies can experience increased sensitivity to INVEGA TRINZA. Manifestations can include confusion, obtundation, postural instability with frequent falls, extrapyramidal symptoms, and clinical features consistent with neuroleptic malignant syndrome.

10 OVERDOSAGE

10.1 Human Experience

No cases of overdose were reported in premarketing studies with paliperidone palmitate injection. Because INVEGA TRINZA is to be administered by healthcare professionals, the potential for overdosage by patients is low.

While experience with paliperidone overdose is limited, among the few cases of overdose reported in premarketing trials with oral paliperidone, the highest estimated ingestion was 405 mg. Observed signs and symptoms included extrapyramidal symptoms and gait unsteadiness. Other potential signs and symptoms include those resulting from an exaggeration of paliperidone's known pharmacological effects, i.e., drowsiness and sedation, tachycardia and hypotension, and QT prolongation. Torsades de pointes and ventricular fibrillation have been reported in a patient in the setting of overdose with oral paliperidone.

Paliperidone is the major active metabolite of risperidone. Overdose experience reported with risperidone can be found in the OVERDOSAGE section of the risperidone package insert.

10.2 Management of Overdosage

Contact a Certified Poison Control Center for the most up to date information on the management of paliperidone and INVEGA TRINZA overdosage (1-800-222-1222 or www.poison.org). Provide supportive care, including close medical supervision and monitoring. Treatment should consist of general measures employed in the management of overdosage with any drug. Consider the possibility of multiple drug overdosage. Ensure an adequate airway, oxygenation, and ventilation. Monitor cardiac rhythm and vital signs. Use supportive and symptomatic measures. There is no specific antidote to paliperidone.

Consider the prolonged-release characteristics of INVEGA TRINZA and the long apparent half-life of paliperidone when assessing treatment needs and recovery.

9 DRUG ABUSE AND DEPENDENCE

9.1 Controlled Substance

INVEGA TRINZA (paliperidone) is not a controlled substance.

9.2 Abuse

Paliperidone has not been systematically studied in animals or humans for its potential for abuse.

9.3 Dependence

Paliperidone has not been systematically studied in animals or humans for its potential for tolerance or physical dependence.

11 DESCRIPTION

INVEGA TRINZA® contains paliperidone palmitate. The active ingredient, paliperidone, is an atypical antipsychotic belonging to the chemical class of benzisoxazole derivatives. INVEGA TRINZA contains a racemic mixture of (+)- and (-)- paliperidone palmitate. The chemical name is (9 RS)-3-[2-[4-(6-Fluoro-1,2-benzisoxazol-3-yl)piperidin-1-yl]ethyl]-2-methyl-4-oxo-6,7,8,9-tetrahydro-4 H-pyrido [1,2- a] pyrimadin-9-yl hexadecanoate. Its molecular formula is C39H57FN4O4 and its molecular weight is 664.89. The structural formula is:

Paliperidone palmitate is very slightly soluble in ethanol and methanol, practically insoluble in polyethylene glycol 400 and propylene glycol, and slightly soluble in ethyl acetate.

INVEGA TRINZA is available as a white to off-white sterile aqueous extended-release suspension for intramuscular injection in dose strengths of 273 mg, 410 mg, 546 mg, and 819 mg paliperidone palmitate in single-dose prefilled syringes. The drug product hydrolyzes to the active moiety, paliperidone, resulting in dose strengths of 175 mg, 263 mg, 350 mg, and 525 mg of paliperidone, respectively. The inactive ingredients are polysorbate 20 (10 mg/mL), polyethylene glycol 4000 (75 mg/mL), citric acid monohydrate (7.5 mg/mL), sodium dihydrogen phosphate monohydrate (6 mg/mL), sodium hydroxide (5.4 mg/mL used as an alkalizing agent to set the pH at 7), and water for injection.

INVEGA TRINZA is provided in a single-dose prefilled syringe (cyclic-olefin-copolymer) with either 175 mg (0.875 mL), 263 mg (1.315 mL), 350 mg (1.75 mL), or 525 mg (2.625 mL) paliperidone (as 273 mg, 410 mg, 546 mg, or 819 mg paliperidone palmitate) suspension with a plunger stopper and tip cap (bromobutyl rubber), a backstop, and 2 types of commercially available needles: a thin walled 22G, 1 ½-inch safety needle and a thin walled 22G, 1-inch safety needle.

12 CLINICAL PHARMACOLOGY

12.1 Mechanism of Action

Paliperidone palmitate is hydrolyzed to paliperidone [see Clinical Pharmacology (12.3)] . Paliperidone is the major active metabolite of risperidone. The mechanism of action of paliperidone is unclear. However, the drug's therapeutic effect in schizophrenia could be mediated through a combination of central dopamine Type 2 (D2) and serotonin Type 2 (5HT2A) receptor antagonism.

12.2 Pharmacodynamics

In vitro, paliperidone acts as an antagonist at the central dopamine Type 2 (D2) and serotonin Type 2 (5HT2A) receptors with binding affinities (Ki values) of 1.6–2.8 nM for D2 and 0.8–1.2 nM for 5HT2A receptors. Paliperidone is also active as an antagonist at histamine H1 and α1 and α2 adrenergic receptors with binding affinities of 32 nM, 4 nM, 17 nM, respectively. Paliperidone has no affinity for cholinergic muscarinic or β1- and β2-adrenergic receptors. The pharmacological activity of the (+)- and (-)- paliperidone enantiomers is qualitatively and quantitatively similar.

12.3 Pharmacokinetics

Absorption and Distribution

Due to its extremely low water solubility, the 3-month formulation of paliperidone palmitate dissolves slowly after intramuscular injection before being hydrolyzed to paliperidone and absorbed into the systemic circulation. The release of the drug starts as early as day 1 and lasts for as long as 18 months.

Following a single intramuscular dose of INVEGA TRINZA, the plasma concentrations of paliperidone gradually rise to reach maximum plasma concentrations at a median Tmax of 30–33 days. Following intramuscular injection of INVEGA TRINZA at doses of 273–819 mg in the deltoid muscle, on average, an 11–12% higher Cmax was observed compared with injection in the gluteal muscle. The release profile and dosing regimen of INVEGA TRINZA results in sustained therapeutic concentrations over 3 months. The total and peak exposure of paliperidone following INVEGA TRINZA administration was dose-proportional over a 273–819 mg dose range. The mean steady-state peak:trough ratio for a INVEGA TRINZA dose was 1.6 following gluteal administration and 1.7 following deltoid administration. Following administration of INVEGA TRINZA, the apparent volume of distribution of paliperidone is 1960 L.

The plasma protein binding of racemic paliperidone is 74%.

Following administration of INVEGA TRINZA, the (+) and (-) enantiomers of paliperidone interconvert, reaching an AUC (+) to (-) ratio of approximately 1.7–1.8.

Metabolism and Elimination

In a study with oral immediate-release^14C-paliperidone, one week following administration of a single oral dose of 1 mg immediate-release^14C-paliperidone, 59% of the dose was excreted unchanged into urine, indicating that paliperidone is not extensively metabolized in the liver. Approximately 80% of the administered radioactivity was recovered in urine and 11% in the feces. Four metabolic pathways have been identified in vivo, none of which accounted for more than 10% of the dose: dealkylation, hydroxylation, dehydrogenation, and benzisoxazole scission. Although in vitro studies suggested a role for CYP2D6 and CYP3A4 in the metabolism of paliperidone, there is no evidence in vivo that these isozymes play a significant role in the metabolism of paliperidone. Population pharmacokinetics analyses indicated no discernible difference on the apparent clearance of paliperidone after administration of oral paliperidone between extensive metabolizers and poor metabolizers of CYP2D6 substrates.

The median apparent half-life of paliperidone following INVEGA TRINZA administration over the dose range of 273–819 mg ranged from 84–95 days following deltoid injections and 118–139 days following gluteal injections. The concentration of paliperidone remaining in the circulation 18 months after dosing of 819 mg INVEGA TRINZA is stopped is estimated to be 3% (following deltoid injection) or 7% (following gluteal injection) of the average steady-state levels.

Long-acting 3-month paliperidone palmitate injection versus other paliperidone formulations

INVEGA TRINZA is designed to deliver paliperidone over a 3-month period, while 1-month paliperidone palmitate injection is administered on a monthly basis. INVEGA TRINZA, when administered at doses that are 3.5-fold higher than the corresponding dose of 1-month paliperidone palmitate injection, results in paliperidone exposures similar to those obtained with corresponding monthly doses of 1-month paliperidone palmitate injection and corresponding once daily doses of paliperidone extended-release tablets. The exposure range for INVEGA TRINZA is encompassed within the exposure range for the approved dose strengths of paliperidone extended-release tablets.

The between-subject variability for paliperidone pharmacokinetics following delivery from INVEGA TRINZA was similar to the variability for paliperidone extended-release tablets. Because of the difference in median pharmacokinetic profiles among the three formulations, caution should be exercised when making a direct comparison of their pharmacokinetic properties.

Drug Interaction Studies

No specific drug interaction studies have been performed with INVEGA TRINZA. The information below is obtained from studies with oral paliperidone.

Effects of other drugs on the exposures of INVEGA TRINZA are summarized in Figure 1. After oral administration of 20 mg/day of paroxetine (a potent CYP2D6 inhibitor), an increase in mean Cmax and AUC values at steady-state was observed (see Figure 1). Higher doses of paroxetine have not been studied. The clinical relevance is unknown. After oral administration, a decrease in mean Cmax and AUC values at steady state is expected when patients are treated with carbamazepine, a strong inducer of both CYP3A4 and P-gp [see Drug Interactions (7.1)] . This decrease is caused, to a substantial degree, by a 35% increase in renal clearance of paliperidone.

Figure 1: The effects of other drugs on INVEGA TRINZA pharmacokinetics.

In vitro studies indicate that CYP2D6 and CYP3A4 may be involved in paliperidone metabolism, however, there is no evidence in vivo that inhibitors of these enzymes significantly affect the metabolism of paliperidone; they contribute to only a small fraction of total body clearance. In vitro studies demonstrated that paliperidone is a substrate of P-glycoprotein (P-gp) [see Drug Interactions (7.2)] .

In vitro studies in human liver microsomes demonstrated that paliperidone does not substantially inhibit the metabolism of drugs metabolized by cytochrome P450 isozymes, including CYP1A2, CYP2A6, CYP2C8/9/10, CYP2D6, CYP2E1, CYP3A4, and CYP3A5. Therefore, paliperidone is not expected to inhibit clearance of drugs that are metabolized by these metabolic pathways in a clinically relevant manner. Paliperidone is also not expected to have enzyme inducing properties.

Paliperidone is a weak inhibitor of P-gp at high concentrations. No in vivo data are available, and the clinical relevance is unknown.

The effects of INVEGA TRINZA on the exposures of other drugs are summarized in Figure 2.

After oral administration of paliperidone, the steady-state Cmax and AUC of valproate were not affected in 13 patients stabilized on valproate. In a clinical study, subjects on stable doses of valproate had comparable valproate average plasma concentrations when oral paliperidone extended-release tablets 3–15 mg/day was added to their existing valproate treatment [see Drug Interactions (7.1)] .

Figure 2: The effects of INVEGA TRINZA on pharmacokinetics of other drugs.

Studies in Specific Populations

No specific pharmacokinetic studies have been performed with INVEGA TRINZA in specific populations. All the information is obtained from studies with oral paliperidone or is based on the population pharmacokinetic modelling of oral paliperidone and INVEGA TRINZA. Exposures of paliperidone in specific populations (renal impairment, hepatic impairment and elderly) are summarized in Figure 3 [see Dosage and Administration (2.5) and Use in Specific Populations (8.6)] .

After oral administration of paliperidone in patients with moderate hepatic impairment, the plasma concentrations of free paliperidone were similar to those of healthy subjects, although total paliperidone exposure decreased because of a decrease in protein binding. Paliperidone has not been studied in patients with severe hepatic impairment [see Use in Specific Populations (8.7)] .

After oral administration of paliperidone in elderly subjects, the Cmax and AUC increased 1.2-fold compared to young subjects. However, there may be age-related decreases in creatinine clearance [see Dosage and Administration (2.5) and Use in Specific Populations (8.5)] .

Figure 3: Effects of intrinsic factors on paliperidone pharmacokinetics.

Based on in vitro studies utilizing human liver enzymes, paliperidone is not a substrate for CYP1A2; smoking should, therefore, not have an effect on the pharmacokinetics of paliperidone. Slower absorption was observed in females in a population pharmacokinetic analysis. At apparent steady-state with INVEGA TRINZA, the trough concentrations were similar between males and females.

Lower Cmax was observed in overweight and obese subjects. At apparent steady-state with INVEGA TRINZA, the trough concentrations were similar among normal, overweight, and obese subjects.

13 NONCLINICAL TOXICOLOGY

13.1 Carcinogenesis, Mutagenesis, Impairment of Fertility

Carcinogenesis

No carcinogenicity studies were conducted with the 3-month paliperidone palmitate extended-release injectable suspension.

The carcinogenic potential of intramuscularly injected 1-month paliperidone palmitate extended-release injectable suspension was assessed in rats. There was an increase in mammary gland adenocarcinomas in female rats at 16, 47, and 94 mg/kg/month, which is 0.2, 0.6, and 1 times, respectively, the MRHD of 819 mg of INVEGA TRINZA based on mg/m^2 body surface area. A no-effect dose was not established. Male rats showed an increase in mammary gland adenomas, fibroadenomas, and carcinomas at 0.6 and 1 times the MRHD based on mg/m^2 body surface area. A carcinogenicity study in mice has not been conducted with paliperidone palmitate.

Carcinogenicity studies with risperidone, which is extensively converted to paliperidone in rats, mice, and humans, were conducted in Swiss albino mice and Wistar rats. Risperidone was administered in the diet at daily doses of 0.63, 2.5, and 10 mg/kg for 18 months to mice and for 25 months to rats. A maximum tolerated dose was not achieved in male mice. There were statistically significant increases in pituitary gland adenomas, endocrine pancreas adenomas, and mammary gland adenocarcinomas. The no-effect dose for these tumors was less than or equal to the maximum recommended human dose of risperidone based on mg/m^2 body surface area (see risperidone package insert). An increase in mammary, pituitary, and endocrine pancreas neoplasms has been found in rodents after chronic administration of other antipsychotic drugs and is considered to be mediated by prolonged dopamine D2 antagonism and hyperprolactinemia. The relevance of these tumor findings in rodents to human risk is unclear [see Warnings and Precautions (5.7)].

Mutagenesis

No mutagenesis studies were conducted with the 3-month paliperidone palmitate extended-release injectable suspension.

Paliperidone palmitate showed no genotoxicity in the in vitro Ames bacterial reverse mutation test or the mouse lymphoma assay. Paliperidone was not genotoxic in the in vitro Ames bacterial reverse mutation test, the mouse lymphoma assay or the in vivo rat bone marrow micronucleus test.

Impairment of Fertility

No fertility studies were conducted with the 3-month paliperidone palmitate extended-release injectable suspension.

In an oral paliperidone study of fertility, the percentage of treated female rats that became pregnant was not affected at oral doses of paliperidone of up to 2.5 mg/kg/day which is 2 times the MRHD based on mg/m^2 body surface area. However, pre- and post-implantation loss was increased, and the number of live embryos was slightly decreased, at 2.5 mg/kg, a dose that also caused slight maternal toxicity. These parameters were not affected at a dose of 0.63 mg/kg, which is half of the MRHD based on mg/m^2 body surface area.

The fertility of male rats was not affected at oral doses of paliperidone of up to 2 times the MRHD of 12 mg/day based on mg/m^2 body surface area, although sperm count and sperm viability studies were not conducted with paliperidone. In a subchronic study in Beagle dogs with risperidone, which is extensively converted to paliperidone in dogs and humans, all doses tested (0.31 mg/kg – 5.0 mg/kg) resulted in decreases in serum testosterone and in sperm motility and concentration (0.6 to 10 times the MRHD of 16 mg/day for risperidone, based on mg/m^2 body surface area). Serum testosterone and sperm parameters partially recovered, but remained decreased after the last observation (two months after treatment was discontinued).

13.2 Animal Toxicology and/or Pharmacology

Injection site toxicity was assessed in minipigs injected intramuscularly with the 3-month paliperidone palmitate extended-release injectable suspension at doses up to 819 mg, which is equal to the MRHD. Injection site inflammatory reactions were greater and more advanced than reactions to the 1-month paliperidone palmitate extended-release injectable suspension. Reversibility of these findings was not examined.

16 HOW SUPPLIED/STORAGE AND HANDLING

INVEGA TRINZA® is available as a white to off-white sterile aqueous extended-release suspension for intramuscular injection in dose strengths of 273 mg/0.88 mL, 410 mg/1.32 mL, 546 mg/1.75 mL, and 819 mg/2.63 mL paliperidone palmitate in single-dose prefilled syringes. The single-use kit contains a prefilled syringe and 2 safety needles (a thin walled 22G, 1-inch safety needle and a thin walled 22G, 1½-inch safety needle).

273 mg paliperidone palmitate kit (NDC 50458-606-01)

410 mg paliperidone palmitate kit (NDC 50458-607-01)

546 mg paliperidone palmitate kit (NDC 50458-608-01)

819 mg paliperidone palmitate kit (NDC 50458-609-01)

Storage and Handling

Store at room temperature 20°C to 25°C (68°F to 77°F); excursions between 15°C and 30°C (59°F and 86°F) are permitted. Do not mix with any other product or diluent.

14 CLINICAL STUDIES

The efficacy of INVEGA TRINZA for the treatment of schizophrenia in patients who have been adequately treated for at least 4 months with INVEGA SUSTENNA (1-month paliperidone palmitate extended-release injectable suspension) was evaluated in a long-term double-blind, placebo-controlled randomized-withdrawal trial designed to evaluate time to relapse involving adult subjects who met DSM-IV-TR criteria for schizophrenia.

Patients could enter the study with acute symptoms (if previously treated with oral antipsychotics) or be clinically stable (if treated with long-acting injectable antipsychotics [LAI]). All patients who previously received oral antipsychotics received the paliperidone palmitate 1-month initiation regimen (deltoid injections of 234 mg and 156 mg one week apart), while those patients switching from LAI medication were treated with the 1-month paliperidone palmitate extended-release injectable suspension in place of the next scheduled injection. Specifically:

- For patients entering the study who were already being treated with the 1-month paliperidone palmitate extended-release injectable suspension, their dosing remained unchanged. Patients who were currently receiving the 39 mg dose of 1-month paliperidone palmitate were not eligible to enroll in the study.
- Patients entering the study who were being treated with 25 mg, 37.5 mg, or 50 mg of RISPERDAL CONSTA (risperidone long-acting injection) were switched to 78 mg, 117 mg, or 156 mg, respectively, of the 1-month paliperidone palmitate administered in the deltoid muscle.
- Patients entering the study who were being treated with any other LAI product were switched to 234 mg of the 1-month paliperidone palmitate administered in the deltoid muscle.

This study consisted of the following three treatment periods:

- A 17-week flexible-dose open-label period with the 1-month paliperidone palmitate (first part of a 29-week open-label stabilization phase). A total of 506 patients entered this phase of the study. Dosing of the 1-month paliperidone palmitate was individualized based on symptom response, tolerability, and previous medication history. Specifically, the dose could be adjusted at the week 5 and 9 injections and the injection site could be deltoid or gluteal. The week 13 dose had to be the same as the week 9 dose. Patients had to be clinically stable at the end of this period before receiving INVEGA TRINZA at the week 17 visit. Clinical stability was defined as achieving a PANSS total score <70 at week 17. The PANSS is a 30-item scale that measures positive symptoms of schizophrenia (7 items), negative symptoms of schizophrenia (7 items), and general psychopathology (16 items), each rated on a scale of 1 (absent) to 7 (extreme); total PANSS scores range from 30 to 210.
- A 12-week open-label treatment period with INVEGA TRINZA (second part of a 29-week open-label stabilization phase). A total of 379 patients received a single-dose of INVEGA TRINZA which was a 3.5 multiple of the last dose of the 1-month paliperidone palmitate. Patients had to remain clinically stable before entry into the next period (double-blind). Clinical stability was defined as achieving a PANSS total score <70 and scores of ≤ 4 for seven specific PANSS items.
- A variable length double-blind treatment period. In this period, 305 stabilized patients were randomized 1:1 to continue treatment with INVEGA TRINZA or placebo until relapse, early withdrawal, or the end of study. Patients were randomized to the same dose of INVEGA TRINZA they received during the open-label phase (i.e., 273 mg, 410 mg, 546 mg, or 819 mg) or to placebo administered every 12 weeks. The numbers (%) of patients entering double-blind on each of the dose levels were 6 (4%) for 273 mg, 15 (9%) for 410 mg, 78 (49%) for 546 mg, and 61 (38%) for 819 mg.

The primary efficacy variable was time to first relapse. Relapse was pre-defined as emergence of one or more of the following: psychiatric hospitalization, ≥ 25% increase (if the baseline score was > 40) or a 10-point increase (if the baseline score was ≤ 40) in total PANSS score on two consecutive assessments, deliberate self-injury, violent behavior, suicidal/homicidal ideation, or a score of ≥ 5 (if the maximum baseline score was ≤ 3) or ≥ 6 (if the maximum baseline score was 4) on two consecutive assessments of the specific PANSS items.

A pre-planned interim analysis showed a statistically significantly longer time to relapse in patients treated with INVEGA TRINZA compared to placebo, and the study was stopped early because efficacy was demonstrated. The most common reason for relapse observed across both treatment groups was increase in the PANSS total score value, followed by psychiatric hospitalization.

Twenty-three percent (23%) of patients in the placebo group and 7.4% of patients in the INVEGA TRINZA group experienced a relapse event. The time to relapse was statistically significantly longer in patients randomized to the INVEGA TRINZA group than compared to placebo-treated patients. A Kaplan-Meier plot of time to relapse by treatment group is shown in Figure 4.

An examination of population subgroups did not reveal any clinically significant differences in responsiveness on the basis of gender, age, or race.

Figure 4: Kaplan-Meier Plot of Cumulative Proportion of Patients with Relapsea Over Time – Interim Analysis.

aThe median time to relapse in the placebo group was 274 days. The median time to relapse in the INVEGA TRINZA group could not be estimated due to low percentage (7.4%) of subjects with relapse.

17 PATIENT COUNSELING INFORMATION

Advise the patient to read the FDA-approved patient labeling (Patient Information).

Neuroleptic Malignant Syndrome (NMS)

Counsel patients about a potentially fatal adverse reaction, Neuroleptic Malignant Syndrome (NMS), that has been reported in association with administration of antipsychotic drugs. Advise patients, family members, or caregivers to contact their healthcare provider or report to the emergency room if they experience signs and symptoms of NMS, including hyperpyrexia, muscle rigidity, altered mental status including delirium, and evidence of autonomic instability (irregular pulse or blood pressure, tachycardia, diaphoresis, and cardiac dysrhythmia) [see Warnings and Precautions (5.3)].

Tardive Dyskinesia

Counsel patients on the signs and symptoms of tardive dyskinesia and to contact their healthcare provider if these abnormal movements occur [see Warnings and Precautions (5.5)].

Metabolic Changes

Educate patients about the risk of metabolic changes, how to recognize symptoms of hyperglycemia and diabetes mellitus, and the need for specific monitoring, including blood glucose, lipids, and weight [see Warnings and Precautions (5.6)].

Orthostatic Hypotension

Educate patients about the risk of orthostatic hypotension and syncope, particularly at the time of initiating treatment, re-initiating treatment, or increasing the dose [see Warnings and Precautions (5.7)] .

Leukopenia/Neutropenia

Advise patients with a pre-existing low WBC or a history of drug induced leukopenia/neutropenia that they should have their CBC monitored while taking INVEGA TRINZA [see Warnings and Precautions (5.9)] .

Hyperprolactinemia

Counsel patients on signs and symptoms of hyperprolactinemia that may be associated with chronic use of INVEGA TRINZA. Advise them to seek medical attention if they experience any of the following: amenorrhea or galactorrhea in females, erectile dysfunction or gynecomastia in males. [See Warnings and Precautions (5.10)]

Interference with Cognitive and Motor Performance

Caution patients about performing activities requiring mental alertness, such as operating hazardous machinery, or operating a motor vehicle until they are reasonably certain that INVEGA TRINZA therapy does not affect them adversely [see Warnings and Precautions (5.11)] .

Priapism

Advise patients of the possibility of painful or prolonged penile erections (priapism). Instruct the patient to seek immediate medical attention in the event of priapism [Warnings and Precautions (5.14)].

Heat Exposure and Dehydration

Counsel patients regarding appropriate care in avoiding overheating and dehydration [see Warnings and Precautions (5.15)] .

Concomitant Medication

Advise patients to inform their healthcare providers if they are taking, or plan to take any prescription or over-the-counter medications, because there is a potential for clinically significant interactions [see Drug Interactions (7)] .

Alcohol

Advise patients to avoid alcohol during treatment with INVEGA TRINZA [see Drug Interactions (7.1)] .

Pregnancy

Advise patients to notify their healthcare provider if they become pregnant or intend to become pregnant during treatment with INVEGA TRINZA. Advise patients that INVEGA TRINZA may cause extrapyramidal and/or withdrawal symptoms in a neonate. Advise patients that there is a pregnancy registry that monitors pregnancy outcomes in women exposed to INVEGA TRINZA during pregnancy [see Use in Specific Populations (8.1)] .

Lactation

Advise breastfeeding women using INVEGA TRINZA to monitor infants for somnolence, failure to thrive, jitteriness, and extrapyramidal symptoms (tremors and abnormal muscle movements) and to seek medical care if they notice these signs [see Use in Specific Populations (8.2)] .

Infertility

Advise females of reproductive potential that INVEGA TRINZA may impair fertility due to an increase in serum prolactin levels. The effects on fertility are reversible [see Use in Specific Populations (8.3)].

INVEGA TRINZA (paliperidone palmitate) Extended-Release Injectable Suspension

INVEGA SUSTENNA, RISPERDAL, and RISPERDAL CONSTA are trademarks of Janssen Pharmaceuticals, Inc.

Manufactured for:
Janssen Pharmaceuticals, Inc.
Titusville, NJ 08560, USA

For patent information: www.janssenpatents.com
© Johnson & Johnson and its affiliates 2015

PATIENT INFORMATION
INVEGA TRINZA ® (in-VAY-guh TRIN-zuh)
(paliperidone palmitate)
Extended-Release Injectable Suspension

What is the most important information I should know about INVEGA TRINZA?
INVEGA TRINZA can cause serious side effects, including:

- Increased risk of death in elderly people who are confused, have memory loss and have lost touch with reality (dementia-related psychosis). INVEGA TRINZA is not for treating dementia-related psychosis.

What is INVEGA TRINZA?
INVEGA TRINZA is a prescription medicine given by injection by a healthcare professional and used to treat schizophrenia.
INVEGA TRINZA is used in people who have been treated with INVEGA SUSTENNA 1 time a month injections for at least 4 months.
It is not known if INVEGA TRINZA is safe and effective in children under 18 years of age.

Who should not receive INVEGA TRINZA?
Do not receive INVEGA TRINZA if you:

- are allergic to paliperidone palmitate, risperidone, or any of the ingredients in INVEGA TRINZA. See the end of this Patient Information leaflet for a complete list of ingredients in INVEGA TRINZA.

What should I tell my healthcare provider before receiving INVEGA TRINZA?
Before you receive INVEGA TRINZA, tell your healthcare provider about all your medical conditions, including if you:

- have had Neuroleptic Malignant Syndrome (NMS)
- have or have had heart problems, including a heart attack, heart failure, abnormal heart rhythm, or long QT syndrome
- have or have had low levels of potassium or magnesium in your blood
- have or have had uncontrolled movements of your tongue, face, mouth, or jaw (tardive dyskinesia)
- have or have had kidney or liver problems
- have diabetes or have a family history of diabetes
- have had a low white blood cell count
- have had problems with dizziness or fainting or are being treated for high blood pressure
- have or have had seizures or epilepsy
- have any other medical conditions
- are pregnant or plan to become pregnant. It is not known if INVEGA TRINZA will harm your unborn baby.
  - If you become pregnant while taking INVEGA TRINZA, talk to your healthcare provider about registering with the National Pregnancy Registry for Atypical Antipsychotics. You can register by calling 1-866-961-2388 or visit http://womensmentalhealth.org/clinical-and-research-programs/pregnancyregistry/.
  - Infants born to women who are treated with INVEGA TRINZA may experience symptoms such as tremors, irritability, excessive sleepiness, eye twitching, muscle spasms, decreased appetite, difficulty breathing, or abnormal movement of arms and legs. Let your healthcare provider know if these symptoms occur.
- are breastfeeding or plan to breastfeed. INVEGA TRINZA can pass into your breast milk. Talk to your healthcare provider about the best way to feed your baby if you receive INVEGA TRINZA.

Tell your healthcare provider about all the medicines you take, including prescription and over-the-counter medicines, vitamins, and herbal supplements.
Know the medicines you take. Keep a list of them to show to your healthcare provider or pharmacist when you get a new medicine.

How will I receive INVEGA TRINZA?

- Follow your INVEGA TRINZA treatment schedule exactly as your healthcare provider tells you to.
- Your healthcare provider will tell you how much INVEGA TRINZA you will receive and when you will receive it.
- INVEGA TRINZA is given as an injection by your healthcare provider into the muscle (intramuscularly) of your arm or your buttocks, 1 time every 3 months.

What should I avoid while receiving INVEGA TRINZA?

- INVEGA TRINZA may affect your ability to make decisions, think clearly, or react quickly. Do not drive, operate heavy machinery, or do other dangerous activities until you know how INVEGA TRINZA affects you.
- Avoid getting overheated or dehydrated.

What are the possible side effects of INVEGA TRINZA?
INVEGA TRINZA may cause serious side effects, including:

- See " What is the most important information I should know about INVEGA TRINZA?"
- stroke in elderly people (cerebrovascular problems) that can lead to death
- Neuroleptic Malignant Syndrome (NMS). NMS is a rare but very serious problem that can happen in people who receive INVEGA TRINZA. NMS can cause death and must be treated in a hospital. Call your healthcare provider right away if you become severely ill and have any of these symptoms:
  - high fever
  - severe muscle stiffness
  - confusion
  - loss of consciousness
  - changes in your breathing, heartbeat and blood pressure
- problems with your heartbeat.These heart problems can cause death. Call your healthcare provider right away if you have any of these symptoms:
  - passing out or feeling like you will pass out
  - dizziness
  - feeling as if your heart is pounding or missing beats
- uncontrolled movements of your tongue, face, mouth, or jaw (tardive dyskinesia)
- metabolic changes. Metabolic changes may include high blood sugar (hyperglycemia), diabetes mellitus and changes in the fat levels in your blood (dyslipidemia), and weight gain.
- low blood pressure and fainting
- changes in your blood cell counts
- high level of prolactin in your blood (hyperprolactinemia). INVEGA TRINZA may cause a rise in the blood levels of a hormone called prolactin (hyperprolactinemia) that may cause side effects including missed menstrual periods, leakage of milk from the breasts, development of breasts in men, or problems with erection.
- problems thinking clearly and moving your body
- seizures
- difficulty swallowing that can cause food or liquid to get into your lungs
- prolonged or painful erection lasting more than 4 hours. Call your healthcare provider or go to your nearest emergency room right away if you have an erection that lasts more than 4 hours.
- problems with control of your body temperature especially when you exercise a lot or spend time doing things that make you warm. It is important for you to drink water to avoid dehydration.

The most common side effects of INVEGA TRINZAinclude: injection site reactions, weight gain, headache, upper respiratory tract infections, feeling restlessness or difficulty sitting still, slow movements, tremors, stiffness and shuffling walk.
Tell your healthcare provider if you have any side effect that bothers you or does not go away.
These are not all the possible side effects of INVEGA TRINZA. For more information, ask your healthcare provider or pharmacist.
Call your doctor for medical advice about side effects. You may report side effects to FDA at 1-800-FDA-1088.

General information about the safe and effective use of INVEGA TRINZA.
Medicines are sometimes prescribed for purposes other than those listed in a Patient Information leaflet. Do not use INVEGA TRINZA for a condition for which it was not prescribed. Do not give INVEGA TRINZA to other people, even if they have the same symptoms that you have. It may harm them. You can ask your pharmacist or healthcare provider for information about INVEGA TRINZA that is written for health professionals.
This Patient Information leaflet summarizes the most important information about INVEGA TRINZA. If you would like more information, talk with your healthcare provider.
You can ask your healthcare provider or pharmacist for more information that is written for healthcare professionals. For more information, go to www.invegatrinzahcp.com or call 1-800-526-7736.

What are the ingredients in INVEGA TRINZA?
Active ingredient : paliperidone palmitate
Inactive ingredients: polysorbate 20, polyethylene glycol 4000, citric acid monohydrate, sodium dihydrogen phosphate monohydrate, sodium hydroxide, and water for injection
Manufactured for: Janssen Pharmaceuticals, Inc., Titusville, NJ 08560, USA
For patent information: www.janssenpatents.com
© Johnson & Johnson and its affiliates 2015

This Patient Information has been approved by the U.S. Food and Drug Administration.

Revised: January 2025

Instructions for Use

INVEGA TRINZA®
paliperidone palmitate extended-release injectable suspension

Administer every 3 months

Shake syringe vigorously for at least 15 seconds

For intramuscular injection only.

Do not administer by any other route.

Important

INVEGA TRINZA should be administered by a healthcare professional as a single injection. DO NOT divide dose into multiple injections.

INVEGA TRINZA is intended for intramuscular use only. Inject slowly, deep into the muscle taking care to avoid injection into a blood vessel.

Read complete instructions prior to use.

Dosing

This medication should be administered once every 3 months.

Preparation

Peel off tab label from the syringe and place in patient record.

INVEGA TRINZA requires longer and more vigorous shaking than INVEGA SUSTENNA (1-month paliperidone palmitate extended-release injectable suspension). Shake the syringe vigorously, with the syringe tip pointing up, for at least 15 seconds within 5 minutes prior to administration (see Step 2).

Thin Wall Safety Needle Selection

Thin wall safety needles are designed to be used with INVEGA TRINZA. Therefore, it is important to only use the needles provided in the INVEGA TRINZA kit.

Dose pack contents

Prefilled Syringe

Thin Wall Safety Needles

1 Select needle

Needle selection is determined by injection area and patient weight.

If administering a Deltoid injection
If patient weighs:
Less than 90 kg
pink hub

If administering a Gluteal injection
If patient weighs:
Less than 90 kg
yellow hub

90 kg or more
yellow hub

90 kg or more
yellow hub

2 Prepare for injection

Check suspension

After shaking the syringe for at least 15 seconds, check the liquid in the viewing window.

The suspension should appear uniform and milky white in color.

It is also normal to see small air bubbles.

Open needle pouch and remove cap

First, open needle pouch by peeling the cover back half way. Place on a clean surface.

Then, holding the syringe upright, twist and pull the rubber cap to remove.

Grasp needle pouch

Fold back needle cover and plastic tray. Then, firmly grasp the needle sheath through the pouch, as shown.

Attach needle

Hold the syringe pointing up. Attach the safety needle to the syringe using a gentle twisting motion to avoid needle hub cracks or damage. Always check for signs of damage or leakage prior to administration.

Remove needle sheath

Pull the needle sheath away from the needle in a straight motion.

Do not twist the sheath, as this may loosen the needle from the syringe.

Remove air bubbles

Hold the syringe upright and tap gently to make any air bubbles rise to the top.

Remove air by pressing the plunger rod upward carefully until a drop of liquid comes out of the needle tip.

3 Inject

Inject dose

Slowly inject the entire contents of the syringe intramuscularly, deep into the selected deltoid or gluteal muscle.

Do not administer by any other route.

4 After injection

Secure needle

After the injection is complete, use your thumb or a flat surface to secure the needle in the safety device.

The needle is secure when a "click" sound is heard.

Dispose properly

Dispose of the syringe and unused needle in an approved sharps container.

Manufactured for:

Janssen Pharmaceuticals, Inc.

Titusville, NJ 08560, USA

For patent information: www.janssenpatents.com

© Johnson & Johnson and its affiliates 2015

This Instructions for Use has been approved by the U.S. Food and Drug Administration. Revised: 2/2025

PRINCIPAL DISPLAY PANEL - 273 mg Syringe Carton

3
MONTHS

Administer
every
3 months

Shake syringe
vigorously for at
least 15 seconds

273 mg

Each single-dose prefilled syringe contains
273 mg (0.88 mL) paliperidone palmitate.

NDC 50458-606-01
Single-dose prefilled syringe. Use entire contents of syringe.

INVEGA TRINZA®273 mg
paliperidone palmitate
extended-release injectable suspension

FOR INTRAMUSCULAR INJECTION ONLY
Each injection must be administered only by
a health care professional.
Shake before using

CONTENTS: 1 single-dose prefilled syringe and 2 needles
(a 22G, 1-inch thin wall safety needle and a 22G,
1½-inch thin wall safety needle)

For recommended dosing instructions, please see
accompanying full Package Insert.
Rx only

Store at room temperature
20°C to 25°C; (68°F to 77°F);
excursions between 15°C to 30°C
(59°F to 86°F) are permitted.

janssen

PRINCIPAL DISPLAY PANEL - 410 mg Syringe Carton

3
MONTHS

Administer
every
3 months

Shake syringe
vigorously for at
least 15 seconds

410 mg

Each single-dose prefilled syringe contains
410 mg (1.32 mL) paliperidone palmitate.

NDC 50458-607-01
Single-dose prefilled syringe. Use entire contents of syringe.

INVEGA TRINZA®410 mg
paliperidone palmitate
extended-release injectable suspension

FOR INTRAMUSCULAR INJECTION ONLY
Each injection must be administered only by
a health care professional.
Shake before using

CONTENTS: 1 single-dose prefilled syringe and 2 needles
(a 22G, 1-inch thin wall safety needle and a 22G,
1½-inch thin wall safety needle)

For recommended dosing instructions, please see
accompanying full Package Insert.
Rx only

Store at room temperature
20°C to 25°C; (68°F to 77°F);
excursions between 15°C to 30°C
(59°F to 86°F) are permitted.

janssen

PRINCIPAL DISPLAY PANEL - 546 mg Syringe Carton

3
MONTHS

Administer
every
3 months

Shake syringe
vigorously for at
least 15 seconds

546 mg

Each single-dose prefilled syringe contains
546 mg (1.75 mL) paliperidone palmitate.

NDC 50458-608-01
Single-dose prefilled syringe. Use entire contents of syringe.

INVEGA TRINZA®546 mg
paliperidone palmitate
extended-release injectable suspension

FOR INTRAMUSCULAR INJECTION ONLY
Each injection must be administered only by
a health care professional.
Shake before using

CONTENTS: 1 single-dose prefilled syringe and 2 needles
(a 22G, 1-inch thin wall safety needle and a 22G,
1½-inch thin wall safety needle)

For recommended dosing instructions, please see
accompanying full Package Insert.
Rx only

Store at room temperature
20°C to 25°C; (68°F to 77°F);
excursions between 15°C to 30°C
(59°F to 86°F) are permitted.

janssen

PRINCIPAL DISPLAY PANEL - 819 mg Syringe Carton

3
MONTHS

Administer
every
3 months

Shake syringe
vigorously for at
least 15 seconds

819 mg

Each single-dose prefilled syringe contains
819 mg (2.63 mL) paliperidone palmitate.

NDC 50458-609-01
Single-dose prefilled syringe. Use entire contents of syringe.

INVEGA TRINZA®819 mg
paliperidone palmitate
extended-release injectable suspension

FOR INTRAMUSCULAR INJECTION ONLY
Each injection must be administered only by
a health care professional.
Shake before using

CONTENTS: 1 single-dose prefilled syringe and 2 needles
(a 22G, 1-inch thin wall safety needle and a 22G,
1½-inch thin wall safety needle)

For recommended dosing instructions, please see
accompanying full Package Insert.
Rx only

Store at room temperature
20°C to 25°C; (68°F to 77°F);
excursions between 15°C to 30°C
(59°F to 86°F) are permitted.

janssen